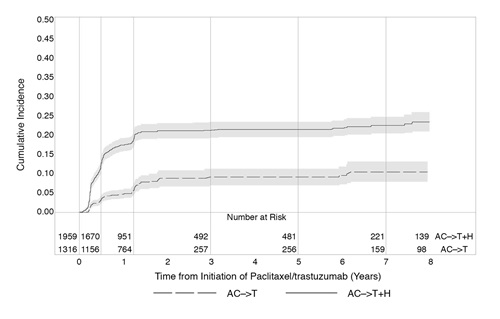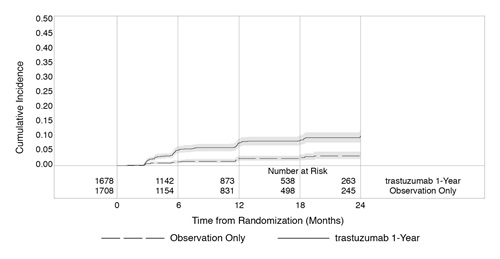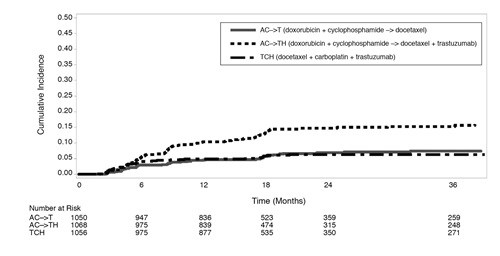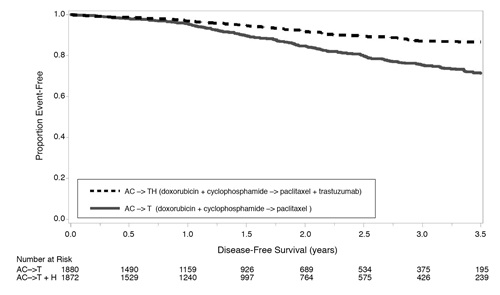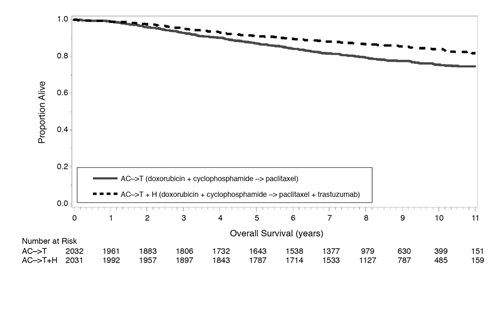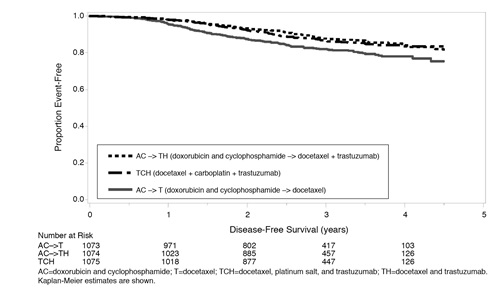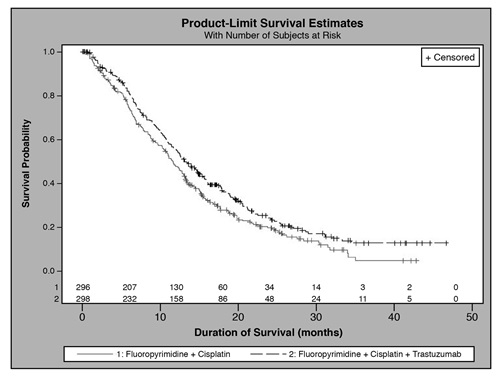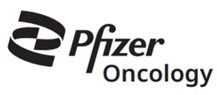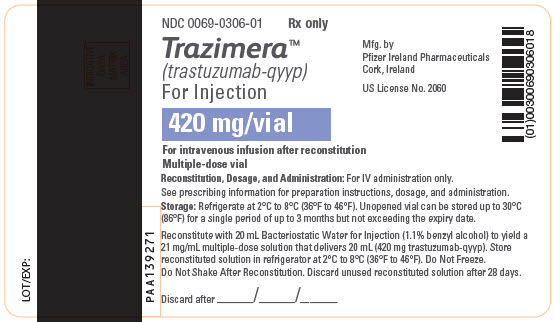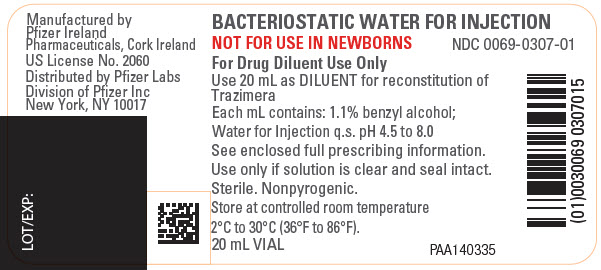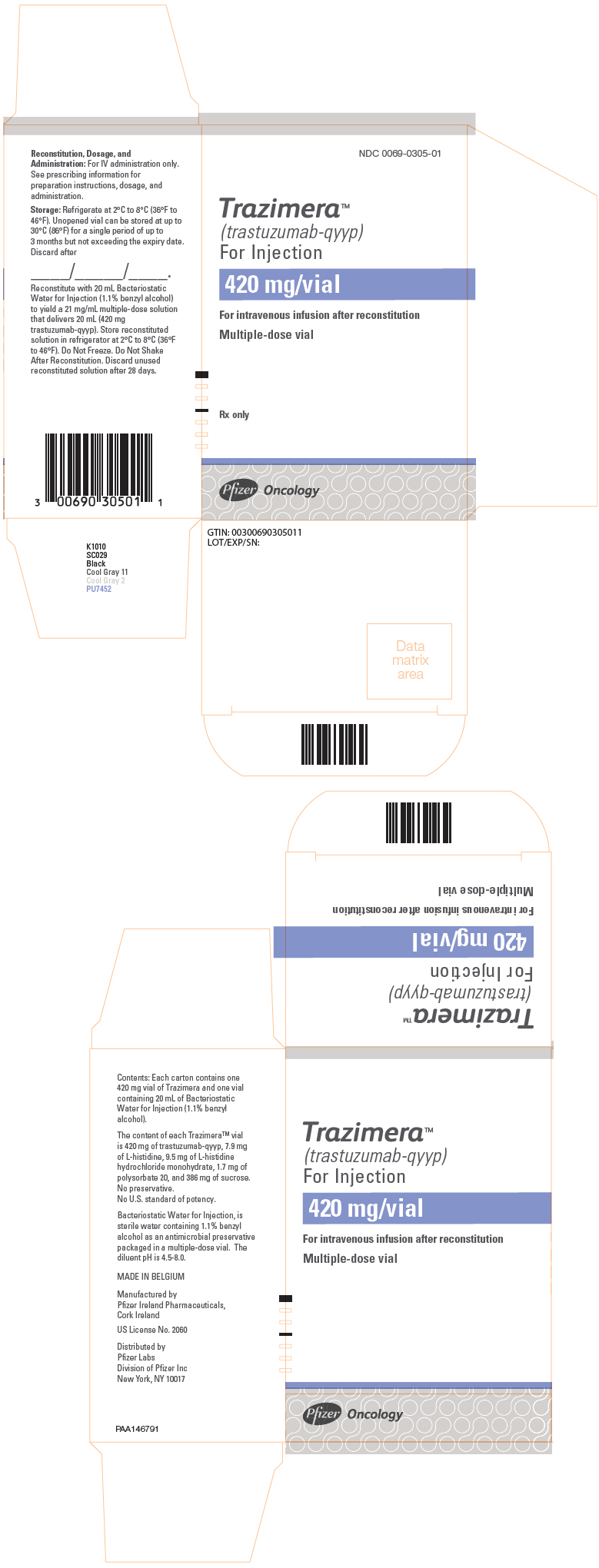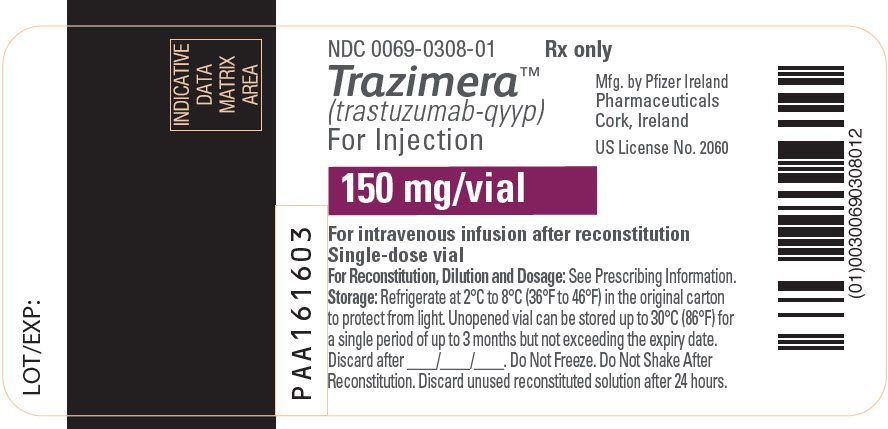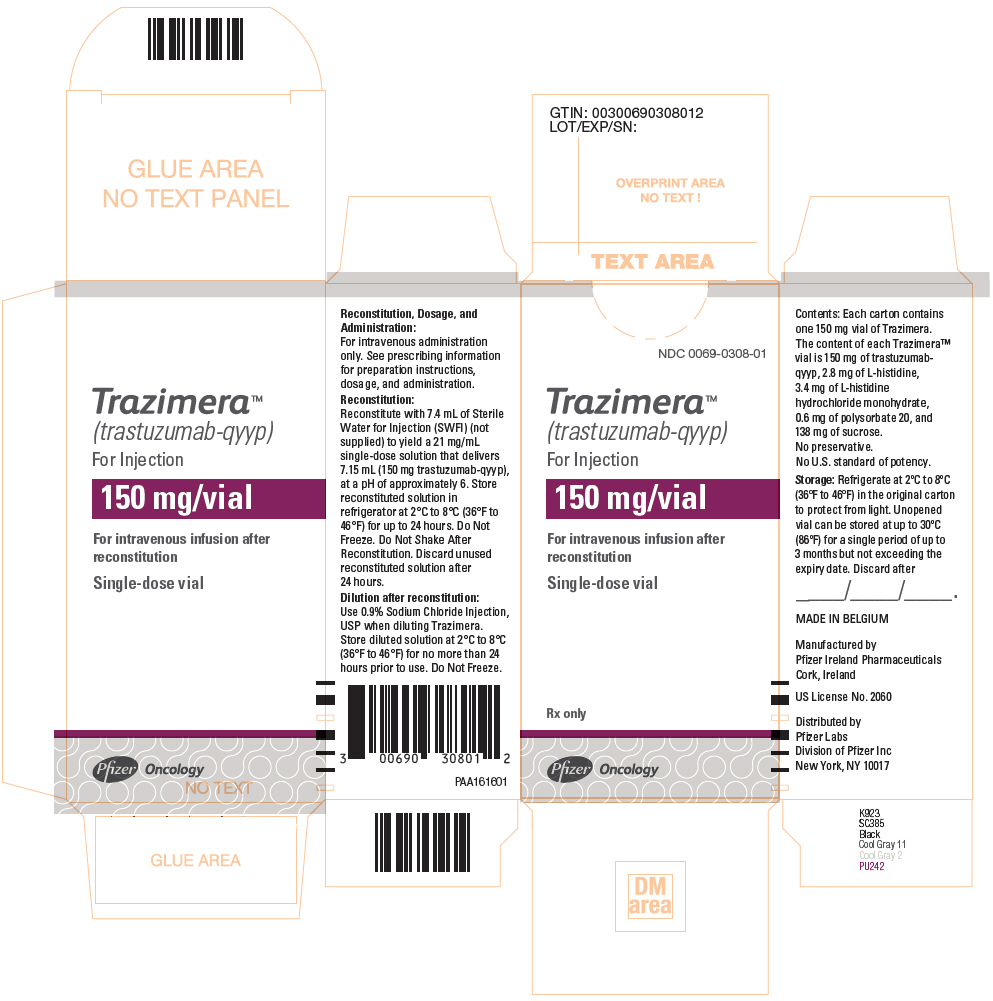 DRUG LABEL: Trazimera
NDC: 0069-0305 | Form: KIT | Route: INTRAVENOUS
Manufacturer: Pfizer Laboratories Div Pfizer Inc
Category: prescription | Type: HUMAN PRESCRIPTION DRUG LABEL
Date: 20250902

ACTIVE INGREDIENTS: TRASTUZUMAB 420 mg/20 mL
INACTIVE INGREDIENTS: SUCROSE 386 mg/20 mL; HISTIDINE MONOHYDROCHLORIDE MONOHYDRATE 9.5 mg/20 mL; HISTIDINE 7.9 mg/20 mL; POLYSORBATE 20 1.7 mg/20 mL; WATER; BENZYL ALCOHOL

HIGHLIGHTS OF PRESCRIBING INFORMATION

These highlights do not include all the information needed to use TRAZIMERA safely and effectively. See full prescribing information for TRAZIMERA.
TRAZIMERA™ (trastuzumab-qyyp) for injection, for intravenous use
Initial U.S. Approval: 2019
TRAZIMERA (trastuzumab-qyyp) is biosimilar [Biosimilar means that the biological product is approved based on data demonstrating that it is highly similar to an FDA-approved biological product, known as a reference product, and that there are no clinically meaningful differences between the biosimilar product and the reference product. Biosimilarity of TRAZIMERA has been demonstrated for the condition(s) of use (e.g., indication(s), dosing regimen(s)), strength(s), dosage form(s), and route(s) of administration described in its Full Prescribing Information.] to HERCEPTIN (trastuzumab).

WARNING: CARDIOMYOPATHY, INFUSION REACTIONS, EMBRYO-FETAL TOXICITY, and PULMONARY TOXICITY

See full prescribing information for complete boxed warning

Cardiomyopathy: Trastuzumab products can result in subclinical and clinical cardiac failure manifesting as CHF, and decreased LVEF, with greatest risk when administered concurrently with anthracyclines. Evaluate cardiac function prior to and during treatment. Discontinue TRAZIMERA for cardiomyopathy. (2.5, 5.1)

Infusion Reactions, Pulmonary Toxicity: Discontinue TRAZIMERA for anaphylaxis, angioedema, interstitial pneumonitis, or acute respiratory distress syndrome. (5.2, 5.4)

Embryo-Fetal Toxicity: Exposure to trastuzumab products during pregnancy can result in oligohydramnios, in some cases complicated by pulmonary hypoplasia and neonatal death. Advise patients of these risks and the need for effective contraception. (5.3, 8.1, 8.3)

RECENT MAJOR CHANGES

Dosage and Administration, Evaluation and Testing; Before Initiating TRAZIMERA (2.1) | 8/2025

1 INDICATIONS AND USAGE

TRAZIMERA is a HER2/neu receptor antagonist indicated in adults for:

- The treatment of HER2-overexpressing breast cancer. (1.1, 1.2)
- The treatment of HER2-overexpressing metastatic gastric or gastroesophageal junction adenocarcinoma. (1.3)

Select patients for therapy based on an FDA-approved companion diagnostic for a trastuzumab product. (1, 2.2)

2 DOSAGE AND ADMINISTRATION

For intravenous (IV) infusion only. Do not administer as an intravenous push or bolus. TRAZIMERA has different dosage and administration instructions than subcutaneous trastuzumab products. (2.3)

Do not substitute TRAZIMERA (trastuzumab-qyyp) for or with ado-trastuzumab emtansine or fam-trastuzumab deruxtecan. (2.3)

Perform HER2 testing using FDA-approved tests by laboratories with demonstrated proficiency. (1, 2.2)
Adjuvant Treatment of HER2-Overexpressing Breast Cancer (2.2)

Administer at either:

- Initial dose of 4 mg/kg over 90 minutes intravenous infusion, then 2 mg/kg over 30 minutes intravenous infusion weekly for 12 weeks (with paclitaxel or docetaxel) or 18 weeks (with docetaxel and carboplatin). One week after the last weekly dose of TRAZIMERA, administer 6 mg/kg as an intravenous infusion over 30 to 90 minutes every three weeks to complete a total of 52 weeks of therapy, or
- Initial dose of 8 mg/kg over 90 minutes intravenous infusion, then 6 mg/kg over 30 to 90 minutes intravenous infusion every three weeks for 52 weeks.

Metastatic HER2-Overexpressing Breast Cancer (2.3)

- Initial dose of 4 mg/kg as a 90 minutes intravenous infusion followed by subsequent weekly doses of 2 mg/kg as 30 minutes intravenous infusions.

Metastatic HER2-Overexpressing Gastric Cancer (2.3)

- Initial dose of 8 mg/kg over 90 minutes intravenous infusion, followed by 6 mg/kg over 30 to 90 minutes intravenous infusion every 3 weeks.

3 DOSAGE FORMS AND STRENGTHS

- For Injection: 150 mg lyophilized powder in a single-dose vial for reconstitution. (3)
- For Injection: 420 mg lyophilized powder in a multiple-dose vial for reconstitution. (3)

4 CONTRAINDICATIONS

- None. (4)

5 WARNINGS AND PRECAUTIONS

- Exacerbation of Chemotherapy-Induced Neutropenia. (5.5, 6.1)

6 ADVERSE REACTIONS

Adjuvant Breast Cancer

- Most common adverse reactions (≥ 5%) are headache, diarrhea, nausea, and chills. (6.1)

Metastatic Breast Cancer

- Most common adverse reactions (≥ 10%) are fever, chills, headache, infection, congestive heart failure, insomnia, cough, and rash. (6.1)

Metastatic Gastric Cancer

- Most common adverse reactions (≥ 10%) are neutropenia, diarrhea, fatigue, anemia, stomatitis, weight loss, upper respiratory tract infections, fever, thrombocytopenia, mucosal inflammation, nasopharyngitis, and dysgeusia. (6.1)

To report SUSPECTED ADVERSE REACTIONS, contact Pfizer Inc. at 1-800-438-1985 and www.pfizer.com or FDA at 1-800-FDA-1088 or www.fda.gov/medwatch.

8 USE IN SPECIFIC POPULATIONS

Females and Males of Reproductive Potential: Verify the pregnancy status of females prior to initiation of TRAZIMERA. (8.3)

FULL PRESCRIBING INFORMATION

WARNING: CARDIOMYOPATHY, INFUSION REACTIONS, EMBRYO-FETAL TOXICITY, and PULMONARY TOXICITY

Cardiomyopathy

Administration of trastuzumab products can result in sub-clinical and clinical cardiac failure. The incidence and severity was highest in patients receiving trastuzumab with anthracycline-containing chemotherapy regimens.

Evaluate left ventricular function in all patients prior to and during treatment with TRAZIMERA. Discontinue TRAZIMERA treatment in patients receiving adjuvant therapy and withhold TRAZIMERA in patients with metastatic disease for clinically significant decrease in left ventricular function [see Dosage and Administration (2.5) and Warnings and Precautions (5.1)].

Infusion Reactions; Pulmonary Toxicity

Administration of trastuzumab products can result in serious and fatal infusion reactions and pulmonary toxicity. Symptoms usually occur during or within 24 hours of administration of trastuzumab products. Interrupt TRAZIMERA infusion for dyspnea or clinically significant hypotension. Monitor patients until symptoms completely resolve. Discontinue TRAZIMERA for anaphylaxis, angioedema, interstitial pneumonitis, or acute respiratory distress syndrome [see Warnings and Precautions (5.2, 5.4)].

Embryo-Fetal Toxicity

Exposure to trastuzumab products during pregnancy can result in oligohydramnios and oligohydramnios sequence manifesting as pulmonary hypoplasia, skeletal abnormalities, and neonatal death. Advise patients of these risks and the need for effective contraception [see Warnings and Precautions (5.3) and Use in Specific Populations (8.1, 8.3)].

1 INDICATIONS AND USAGE

1.1 Adjuvant Breast Cancer

TRAZIMERA is indicated in adults for adjuvant treatment of HER2-overexpressing node positive or node negative (ER/PR negative or with one high risk feature [see Clinical Studies (14.1)]) breast cancer

- as part of a treatment regimen consisting of doxorubicin, cyclophosphamide, and either paclitaxel or docetaxel
- as part of a treatment regimen with docetaxel and carboplatin
- as a single agent following multi-modality anthracycline based therapy.

Select patients for therapy based on an FDA-approved companion diagnostic for a trastuzumab product [see Dosage and Administration (2.2)].

1.2 Metastatic Breast Cancer

TRAZIMERA is indicated in adults:

- In combination with paclitaxel for first-line treatment of HER2-overexpressing metastatic breast cancer
- As a single agent for treatment of HER2-overexpressing breast cancer in patients who have received one or more chemotherapy regimens for metastatic disease.

Select patients for therapy based on an FDA-approved companion diagnostic for a trastuzumab product [see Dosage and Administration (2.2)].

1.3 Metastatic Gastric Cancer

TRAZIMERA is indicated in adults, in combination with cisplatin and capecitabine or 5-fluorouracil, for the treatment of patients with HER2-overexpressing metastatic gastric or gastroesophageal junction adenocarcinoma who have not received prior treatment for metastatic disease.

Select patients for therapy based on an FDA-approved companion diagnostic for a trastuzumab product [see Dosage and Administration (2.2)].

2 DOSAGE AND ADMINISTRATION

2.1 Evaluation and Testing Before Initiating TRAZIMERA

Assess left ventricular ejection fraction (LVEF) prior to initiation of TRAZIMERA and at regular intervals during treatment [see Boxed Warning, Dosage and Administration (2.5) and Warnings and Precautions (5.1)].

Verify the pregnancy status of females of reproductive potential prior to the initiation of TRAZIMERA [see Warnings and Precautions (5.3) and Use in Specific Populations (8.1, 8.3)].

2.2 Patient Selection

Select patients based on HER2 protein overexpression or HER2 gene amplification in tumor specimens [see Indications and Usage (1) and Clinical Studies (14)]. Assessment of HER2 protein overexpression and HER2 gene amplification should be performed using FDA-approved tests specific for breast or gastric cancers by laboratories with demonstrated proficiency. Information on the FDA-approved tests for the detection of HER2 protein overexpression and HER2 gene amplification is available at: http://www.fda.gov/CompanionDiagnostics.

Assessment of HER2 protein overexpression and HER2 gene amplification in metastatic gastric cancer should be performed using FDA-approved tests specifically for gastric cancers due to differences in gastric vs. breast histopathology, including incomplete membrane staining and more frequent heterogeneous expression of HER2 seen in gastric cancers.

Improper assay performance, including use of suboptimally fixed tissue, failure to utilize specified reagents, deviation from specific assay instructions, and failure to include appropriate controls for assay validation, can lead to unreliable results.

2.3 Recommended Dosage

- TRAZIMERA is for intravenous infusion only. Do not administer as an intravenous push or bolus.
- TRAZIMERA has different dosage and administration instructions than subcutaneous trastuzumab products.
- Do not mix TRAZIMERA with other drugs.
- Do not substitute TRAZIMERA (trastuzumab-qyyp) for or with ado-trastuzumab emtansine or fam-trastuzumab deruxtecan.

Adjuvant Treatment of Breast Cancer

Administer according to one of the following doses and schedules for a total of 52 weeks of TRAZIMERA therapy:

During and following paclitaxel, docetaxel, or docetaxel and carboplatin:

- Initial dose of 4 mg/kg as an intravenous infusion over 90 minutes then at 2 mg/kg as an intravenous infusion over 30 minutes weekly during chemotherapy for the first 12 weeks (paclitaxel or docetaxel) or 18 weeks (docetaxel and carboplatin).
- One week following the last weekly dose of TRAZIMERA, administer TRAZIMERA at 6 mg/kg as an intravenous infusion over 30 to 90 minutes every three weeks.

As a single agent within three weeks following completion of multi-modality, anthracycline-based chemotherapy regimens:

- Initial dose at 8 mg/kg as an intravenous infusion over 90 minutes.
- Subsequent doses at 6 mg/kg as an intravenous infusion over 30 to 90 minutes every three weeks.
- Extending adjuvant treatment beyond one year is not recommended [see Adverse Reactions (6.1)].

Metastatic Breast Cancer

- Administer TRAZIMERA, alone or in combination with paclitaxel, at an initial dose of 4 mg/kg as a 90-minute intravenous infusion followed by subsequent once weekly doses of 2 mg/kg as 30-minute intravenous infusions until disease progression.

Metastatic Gastric Cancer

- Administer TRAZIMERA at an initial dose of 8 mg/kg as a 90-minute intravenous infusion followed by subsequent doses of 6 mg/kg as an intravenous infusion over 30 to 90 minutes every three weeks until disease progression.

2.4 Important Dosing Considerations

Missed Dose

If the patient has missed a dose of TRAZIMERA by one week or less, then the usual maintenance dose (weekly schedule: 2 mg/kg; once every three weeks schedule: 6 mg/kg) should be administered as soon as possible. Do not wait until the next planned cycle. Subsequent TRAZIMERA maintenance doses should be administered 7 days or 21 days later according to the weekly or once every three weeks schedules, respectively.

If the patient has missed a dose of TRAZIMERA by more than one week, a re-loading dose of TRAZIMERA should be administered over approximately 90 minutes (weekly schedule: 4 mg/kg; once every three weeks schedule: 8 mg/kg) as soon as possible. Subsequent TRAZIMERA maintenance doses (weekly schedule: 2 mg/kg; once every three weeks schedule: 6 mg/kg) should be administered 7 days or 21 days later according to the weekly or once every three weeks schedules, respectively.

2.5 Dosage Modifications for Adverse Reactions

Infusion Reactions

[See Boxed Warning and Warnings and Precautions (5.2)]

- Decrease the rate of infusion for mild or moderate infusion reactions
- Interrupt the infusion in patients with dyspnea or clinically significant hypotension
- Discontinue TRAZIMERA for severe or life-threatening infusion reactions.

Cardiomyopathy

[See Boxed Warning, Warnings and Precautions (5.1)]

Assess left ventricular ejection fraction (LVEF) prior to initiation of TRAZIMERA and at regular intervals during treatment. Withhold TRAZIMERA dosing for at least 4 weeks for either of the following:

- ≥ 16% absolute decrease in LVEF from pre-treatment values
- LVEF below institutional limits of normal and ≥ 10% absolute decrease in LVEF from pretreatment values.

TRAZIMERA may be resumed if, within 4 to 8 weeks, the LVEF returns to normal limits and the absolute decrease from baseline is ≤ 15%.

Permanently discontinue TRAZIMERA for a persistent (> 8 weeks) LVEF decline or for suspension of TRAZIMERA dosing on more than 3 occasions for cardiomyopathy.

2.6 Preparation Instructions

To prevent medication errors, it is important to check the vial labels to ensure that the drug being prepared and administered is TRAZIMERA (trastuzumab-qyyp) and not ado-trastuzumab emtansine or fam-trastuzumab deruxtecan.

420 mg Multiple-Dose Vial

Reconstitution

Reconstitute each 420 mg vial of TRAZIMERA with 20 mL of Bacteriostatic Water for Injection (BWFI) containing 1.1% benzyl alcohol as a preservative to yield a multiple-dose solution containing 21 mg/mL trastuzumab-qyyp that delivers 20 mL (420 mg trastuzumab-qyyp). In patients with known hypersensitivity to benzyl alcohol, reconstitute with 20 mL of Sterile Water for Injection (SWFI) without preservative to yield a one-time use solution.

Use appropriate aseptic technique when performing the following reconstitution steps:

- Using a sterile syringe, slowly inject the 20 mL of diluent into the vial containing the lyophilized powder of TRAZIMERA, which has a cake-like appearance. The reconstituted vial yields a solution for multiple-dose use, containing 21 mg/mL trastuzumab-qyyp.
- Swirl the vial gently to aid reconstitution. DO NOT SHAKE.
- Slight foaming of the product may be present upon reconstitution. Allow the vial to stand undisturbed for approximately 5 minutes.
- Parenteral drug products should be inspected visually for particulate matter and discoloration prior to administration, whenever solution and container permit. Inspect visually for particulates and discoloration. The solution should be free of visible particulates, clear to slightly opalescent and colorless to pale yellow-brown.
- Store reconstituted TRAZIMERA in the refrigerator at 2°C to 8°C (36°F to 46°F); discard unused TRAZIMERA after 28 days. If TRAZIMERA is reconstituted with SWFI without preservative, use immediately and discard any unused portion. Do not freeze.

Dilution

- Determine the dose (mg) of TRAZIMERA [see Dosage and Administration (2.3)].
- Calculate the volume of the 21 mg/mL reconstituted TRAZIMERA solution needed.
- Withdraw this amount from the vial using a sterile needle and syringe and add it to an infusion bag containing 250 mL of 0.9% Sodium Chloride Injection, USP. DO NOT USE DEXTROSE (5%) SOLUTION.
- Gently invert the bag to mix the solution.
- The solution of TRAZIMERA for infusion diluted in polyvinylchloride, polyethylene, polypropylene, or ethylene vinyl acetate bags or glass intravenous bottles containing 0.9% Sodium Chloride Injection, USP, should be stored at 2°C to 8°C (36°F to 46°F) for no more than 24 hours prior to use. This storage time is additional to the time allowed for the reconstituted vials. Do not freeze.

150 mg Single-Dose Vial

Reconstitution

Reconstitute each 150 mg vial of TRAZIMERA with 7.4 mL of Sterile Water for Injection (SWFI) (not supplied) to yield a single-dose solution containing 21 mg/mL trastuzumab-qyyp that delivers 7.15 mL (150 mg trastuzumab-qyyp).

Use appropriate aseptic technique when performing the following reconstitution steps:

- Using a sterile syringe, slowly inject 7.4 mL of SWFI (not supplied) into the vial containing the lyophilized powder of TRAZIMERA, which has a cake-like appearance. The reconstituted vial yields a solution containing 21 mg/mL trastuzumab-qyyp.
- Swirl the vial gently to aid reconstitution. DO NOT SHAKE.
- Slight foaming of the product may be present upon reconstitution. Allow the vial to stand undisturbed for approximately 5 minutes.
- Parenteral drug products should be inspected visually for particulate matter and discoloration prior to administration, whenever solution and container permit. Inspect visually for particulates and discoloration. The solution should be free of visible particulates, clear to slightly opalescent and colorless to pale yellow-brown.
- Use the TRAZIMERA solution immediately following reconstitution with SWFI, as it contains no preservative and is intended for one-time use only. If not used immediately, store the reconstituted TRAZIMERA solution for up to 24 hours at 2°C to 8°C (36°F to 46°F); discard unused TRAZIMERA after 24 hours. Do not freeze.

Dilution

- Determine the dose (mg) of TRAZIMERA [see Dosage and Administration (2.3)].
- Calculate the volume of the 21 mg/mL reconstituted TRAZIMERA solution needed.
- Withdraw this amount from the vial using a sterile needle and syringe and add it to an infusion bag containing 250 mL of 0.9% Sodium Chloride Injection, USP. DO NOT USE DEXTROSE (5%) SOLUTION.
- Gently invert the bag to mix the solution.
- The solution of TRAZIMERA for infusion diluted in polyvinylchloride, polyethylene, polypropylene, or ethylene vinyl acetate bags or glass intravenous bottles containing 0.9% Sodium Chloride Injection, USP, should be stored at 2°C to 8°C (36°F to 46°F) for no more than 24 hours prior to use. Discard after 24 hours. This storage time is additional to the time allowed for the reconstituted vials. Do not freeze.

3 DOSAGE FORMS AND STRENGTHS

- For injection: 150 mg of TRAZIMERA as a white lyophilized powder in a single-dose vial.
- For injection: 420 mg of TRAZIMERA as a white lyophilized powder in a multiple-dose vial.

4 CONTRAINDICATIONS

None.

5 WARNINGS AND PRECAUTIONS

5.1 Cardiomyopathy

Trastuzumab products can cause left ventricular cardiac dysfunction, arrhythmias, hypertension, disabling cardiac failure, cardiomyopathy, and cardiac death [see Boxed Warning]. Trastuzumab products can also cause asymptomatic decline in left ventricular ejection fraction (LVEF).

There is a 4 to 6 fold increase in the incidence of symptomatic myocardial dysfunction among patients receiving trastuzumab products as a single agent or in combination therapy compared with those not receiving trastuzumab products. The highest absolute incidence occurs when a trastuzumab product is administered with an anthracycline.

Withhold TRAZIMERA for ≥ 16% absolute decrease in LVEF from pre-treatment values or an LVEF value below institutional limits of normal and ≥ 10% absolute decrease in LVEF from pretreatment values [see Dosage and Administration (2.5)]. The safety of continuation or resumption of trastuzumab products in patients with trastuzumab product-induced left ventricular cardiac dysfunction has not been studied.

Patients who receive anthracycline after stopping trastuzumab products may also be at increased risk of cardiac dysfunction [see Drug Interactions (7) and Clinical Pharmacology (12.3)].

Cardiac Monitoring

Conduct thorough cardiac assessment, including history, physical examination, and determination of LVEF by echocardiogram or MUGA scan. The following schedule is recommended:

- Baseline LVEF measurement immediately prior to initiation of TRAZIMERA
- LVEF measurements every 3 months during and upon completion of TRAZIMERA
- Repeat LVEF measurement at 4 week intervals if TRAZIMERA is withheld for significant left ventricular cardiac dysfunction [see Dosage and Administration (2.5)]
- LVEF measurements every 6 months for at least 2 years following completion of TRAZIMERA as a component of adjuvant therapy.

In NSABP B31, 15% (158/1031) of patients discontinued trastuzumab due to clinical evidence of myocardial dysfunction or significant decline in LVEF after a median follow-up duration of 8.7 years in the AC-TH (anthracycline, cyclophosphamide, paclitaxel, and trastuzumab) arm. In HERA (one-year trastuzumab treatment), the number of patients who discontinued trastuzumab due to cardiac toxicity at 12.6 months median duration of follow-up was 2.6% (44/1678). In BCIRG006, a total of 2.9% (31/1056) of patients in the TCH (docetaxel, carboplatin, trastuzumab) arm (1.5% during the chemotherapy phase and 1.4% during the monotherapy phase) and 5.7% (61/1068) of patients in the AC-TH arm (1.5% during the chemotherapy phase and 4.2% during the monotherapy phase) discontinued trastuzumab due to cardiac toxicity.

Among 64 patients receiving adjuvant chemotherapy (NSABP B31 and NCCTG N9831) who developed congestive heart failure (CHF), one patient died of cardiomyopathy, one patient died suddenly without documented etiology, and 33 patients were receiving cardiac medication at last follow-up. Approximately 24% of the surviving patients had recovery to a normal LVEF (defined as ≥ 50%) and no symptoms on continuing medical management at the time of last follow-up. Incidence of congestive heart failure is presented in Table 1. The safety of continuation or resumption of trastuzumab products in patients with trastuzumab product-induced left ventricular cardiac dysfunction has not been studied.

Table 1: Incidence of Congestive Heart Failure in Adjuvant Breast Cancer Studies
 |  | Incidence of Congestive Heart Failure % (n)
Study | Regimen | Trastuzumab | Control
NSABP B31 &; NCCTG N9831 [Median follow-up duration for NSABP B31 & NCCTG N9831 combined was 8.3 years in the AC→paclitaxel+trastuzumab arm.] | AC [Anthracycline (doxorubicin) and cyclophosphamide.] → Paclitaxel+Trastuzumab | 3.2% (64/2000) [Includes 1 patient with fatal cardiomyopathy and 1 patient with sudden death without documented etiology.] | 1.3% (21/1655)
HERA [Includes NYHA II-IV and cardiac death at 12.6 months median duration of follow-up in the one-year trastuzumab arm.] | Chemotherapy → Trastuzumab | 2% (30/1678) | 0.3% (5/1708)
BCIRG006 | AC → Docetaxel+Trastuzumab | 2% (20/1068) | 0.3% (3/1050)
BCIRG006 | Docetaxel+Carboplatin+Trastuzumab | 0.4% (4/1056) | 0.3% (3/1050)

In HERA (one-year trastuzumab treatment), at a median follow-up duration of 8 years, the incidence of severe CHF (NYHA III & IV) was 0.8%, and the rate of mild symptomatic and asymptomatic left ventricular dysfunction was 4.6%.

Table 2: Incidence of Cardiac Dysfunction [Congestive heart failure or significant asymptomatic decrease in LVEF.] in Metastatic Breast Cancer Studies
 |  | Incidence
 |  | NYHA I–IV |  | NYHA III–IV
Study | Event | Trastuzumab | Control | Trastuzumab | Control
H0648g (AC) [Anthracycline (doxorubicin or epirubicin) and cyclophosphamide.] | Cardiac Dysfunction | 28% | 7% | 19% | 3%
H0648g (paclitaxel) | Cardiac Dysfunction | 11% | 1% | 4% | 1%
H0649g | Cardiac Dysfunction [Includes 1 patient with fatal cardiomyopathy.] | 7% | N/A | 5% | N/A

In BCIRG006, the incidence of NCI-CTC Grade 3/4 cardiac ischemia/infarction was higher in the trastuzumab containing regimens (AC-TH: 0.3% (3/1068) and TCH: 0.2% (2/1056)) as compared to none in AC-T.

5.2 Infusion Reactions

Infusion reactions consist of a symptom complex characterized by fever and chills, and on occasion included nausea, vomiting, pain (in some cases at tumor sites), headache, dizziness, dyspnea, hypotension, rash, and asthenia [see Adverse Reactions (6.1)].

In post-marketing reports, serious and fatal infusion reactions have been reported. Severe reactions, which include bronchospasm, anaphylaxis, angioedema, hypoxia, and severe hypotension, were usually reported during or immediately following the initial infusion. However, the onset and clinical course were variable, including progressive worsening, initial improvement followed by clinical deterioration, or delayed post-infusion events with rapid clinical deterioration. For fatal events, death occurred within hours to days following a serious infusion reaction.

Interrupt TRAZIMERA infusion in all patients experiencing dyspnea, clinically significant hypotension, and intervention of medical therapy administered (which may include epinephrine, corticosteroids, diphenhydramine, bronchodilators, and oxygen). Patients should be evaluated and carefully monitored until complete resolution of signs and symptoms. Permanent discontinuation should be strongly considered in all patients with severe infusion reactions.

There are no data regarding the most appropriate method of identification of patients who may safely be retreated with trastuzumab products after experiencing a severe infusion reaction. Prior to resumption of trastuzumab infusion, the majority of patients who experienced a severe infusion reaction were pre-medicated with antihistamines and/or corticosteroids. While some patients tolerated trastuzumab infusions, others had recurrent severe infusion reactions despite pre-medications.

5.3 Embryo-Fetal Toxicity

Trastuzumab products can cause fetal harm when administered to a pregnant woman. In post-marketing reports, use of trastuzumab during pregnancy resulted in cases of oligohydramnios and oligohydramnios sequence manifesting as pulmonary hypoplasia, skeletal abnormalities, and neonatal death.

Verify the pregnancy status of females of reproductive potential prior to the initiation of TRAZIMERA. Advise pregnant women and females of reproductive potential that exposure to TRAZIMERA during pregnancy or within 7 months prior to conception can result in fetal harm. Advise females of reproductive potential to use effective contraception during treatment and for 7 months following the last dose of TRAZIMERA [see Use in Specific Populations (8.1, 8.3) and Clinical Pharmacology (12.3)].

5.4 Pulmonary Toxicity

Trastuzumab product use can result in serious and fatal pulmonary toxicity. Pulmonary toxicity includes dyspnea, interstitial pneumonitis, pulmonary infiltrates, pleural effusions, non-cardiogenic pulmonary edema, pulmonary insufficiency and hypoxia, acute respiratory distress syndrome, and pulmonary fibrosis. Such events can occur as sequelae of infusion reactions [see Warnings and Precautions (5.2)]. Patients with symptomatic intrinsic lung disease or with extensive tumor involvement of the lungs, resulting in dyspnea at rest, appear to have more severe toxicity.

5.5 Exacerbation of Chemotherapy-Induced Neutropenia

In randomized, controlled clinical trials, the per-patient incidences of NCI-CTC Grade 3 to 4 neutropenia and of febrile neutropenia were higher in patients receiving trastuzumab in combination with myelosuppressive chemotherapy as compared to those who received chemotherapy alone. The incidence of septic death was similar among patients who received trastuzumab and those who did not [see Adverse Reactions (6.1)].

6 ADVERSE REACTIONS

The following adverse reactions are discussed in greater detail in other sections of the label:

- Cardiomyopathy [see Warnings and Precautions (5.1)]
- Infusion Reactions [see Warnings and Precautions (5.2)]
- Embryo-Fetal Toxicity [see Warnings and Precautions (5.3)]
- Pulmonary Toxicity [see Warnings and Precautions (5.4)]
- Exacerbation of Chemotherapy-Induced Neutropenia [see Warnings and Precautions (5.5)]

6.1 Clinical Trials Experience

Because clinical trials are conducted under widely varying conditions, adverse reaction rates observed in the clinical trials of a drug cannot be directly compared to rates in the clinical trials of another drug and may not reflect the rates observed in practice.

The most common adverse reactions in patients receiving trastuzumab products in the adjuvant and metastatic breast cancer setting are fever, nausea, vomiting, infusion reactions, diarrhea, infections, increased cough, headache, fatigue, dyspnea, rash, neutropenia, anemia, and myalgia. Adverse reactions requiring interruption or discontinuation of trastuzumab product treatment include CHF, significant decline in left ventricular cardiac function, severe infusion reactions, and pulmonary toxicity [see Dosage and Administration (2.5)].

In the metastatic gastric cancer setting, the most common adverse reactions (≥ 10%) that were increased (≥ 5% difference) in the trastuzumab arm as compared to the chemotherapy alone arm were neutropenia, diarrhea, fatigue, anemia, stomatitis, weight loss, upper respiratory tract infections, fever, thrombocytopenia, mucosal inflammation, nasopharyngitis, and dysgeusia. The most common adverse reactions which resulted in discontinuation of treatment on the trastuzumab-containing arm in the absence of disease progression were infection, diarrhea, and febrile neutropenia.

Adjuvant Breast Cancer

The information below reflects exposure to one-year trastuzumab therapy across three randomized, open-label studies, NSABP B31, NCCTG N9831, and HERA, with (n = 3678) or without (n = 3363) trastuzumab in the adjuvant treatment of breast cancer.

HERA

Table 3 reflects exposure to trastuzumab in 1678 patients in HERA; the median treatment duration was 51 weeks and median number of infusions was 18 [see Clinical Studies (14.1)].

Table 3: Adverse Reactions (≥ 1%) in HERA (All Grades) [The incidence of Grade 3 or higher adverse reactions was < 1% in both arms for each listed term.]
Adverse Reactions | Trastuzumab; (n = 1678); % | Observation; (n = 1708); %
Nervous System
Headache | 10 | 3
Paresthesia | 2 | 0.6
Musculoskeletal
Arthralgia | 8 | 6
Back pain | 5 | 3
Myalgia | 4 | 1
Bone pain | 3 | 2
Muscle spasm | 3 | 0.2
Infections
Nasopharyngitis | 8 | 3
Urinary tract infection | 3 | 0.8
Gastrointestinal
Diarrhea | 7 | 1
Nausea | 6 | 1
Vomiting | 3.5 | 0.6
Constipation | 2 | 1
Dyspepsia | 2 | 0.5
Upper abdominal pain | 2 | 1
General
Pyrexia | 6 | 0.4
Peripheral edema | 5 | 2
Chills | 5 | 0
Asthenia | 4.5 | 2
Influenza-like illness | 2 | 0.2
Respiratory Thoracic Mediastinal
Cough | 5 | 2
Influenza | 4 | 0.5
Dyspnea | 3 | 2
URI | 3 | 1
Rhinitis | 2 | 0.4
Pharyngolaryngeal pain | 2 | 0.5
Sinusitis | 2 | 0.3
Epistaxis | 2 | 0.06
Cardiac
Hypertension | 4 | 2
Dizziness | 4 | 2
Ejection fraction decreased | 3.5 | 0.6
Palpitations | 3 | 0.7
Cardiac arrhythmias [Higher level grouping term.] | 3 | 1
Cardiac failure (congestive) | 2 | 0.3
Skin & Subcutaneous Tissue
Rash | 4 | 0.6
Nail disorders | 2 | 0
Pruritus | 2 | 0.6

Clinically relevant adverse reactions in < 1% of patients who received trastuzumab in HERA included hypersensitivity (0.6%), cardiac failure (0.5%), cardiac disorder (0.3%), interstitial pneumonitis (0.2%), pulmonary hypertension (0.2%), ventricular disorder (0.2%), autoimmune thyroiditis (0.3%), and sudden death (0.06%).

Adjuvant Treatment of Breast Cancer with Trastuzumab Beyond One Year

Extending adjuvant treatment beyond one year is not recommended [see Dosage and Administration (2.3)]. In HERA, a comparison of trastuzumab administered once every 3 weeks for two years versus one year was performed. The rate of asymptomatic cardiac dysfunction was increased in the 2-year trastuzumab compared to the 1-year trastuzumab treatment arm (8.1% versus 4.6%, respectively). More patients experienced at least one adverse reaction of Grade 3 or higher in the 2-year trastuzumab treatment arm (20.4%) compared with the one-year trastuzumab treatment arm (16.3%).

NSABP B31 and NCCTG N9831

The safety data from NSABP B31 and NCCTG N9831 were obtained from 3655 patients, of whom 2000 received trastuzumab; the median treatment duration was 51 weeks [see Clinical Studies (14.1)].

In NSABP B31, only Grade 3 to 5 adverse events, treatment-related Grade 2 events, and Grade 2 to 5 dyspnea were collected during and for up to 3 months following protocol-specified treatment. The following non-cardiac adverse reactions of Grade 2 to 5 occurred at an incidence of at least 2% greater among patients receiving trastuzumab plus chemotherapy as compared to chemotherapy alone: fatigue (29.5% vs. 22.4%), infection (24.0% vs. 12.8%), hot flashes (17.1% vs. 15%), anemia (12.3% vs. 6.7%), dyspnea (11.8% vs. 4.6%), rash/desquamation (10.9% vs. 7.6%), leukopenia (10.5% vs. 8.4%), neutropenia (6.4% vs. 4.3%), headache (6.2% vs. 3.8%), pain (5.5% vs. 3%), edema (4.7% vs. 2.7%), and insomnia (4.3% vs. 1.5%). The majority of these events were Grade 2 in severity.

In NCCTG N9831, data collection was limited to the following investigator-attributed treatment-related adverse reactions: NCI-CTC Grade 4 and 5 hematologic toxicities, Grade 3 to 5 non-hematologic toxicities, selected Grade 2 to 5 toxicities associated with taxanes (myalgia, arthralgias, nail changes, motor neuropathy, and sensory neuropathy) and Grade 1 to 5 cardiac toxicities occurring during chemotherapy and/or trastuzumab treatment. The following non-cardiac adverse reactions of Grade 2 to 5 occurred at an incidence of at least 2% greater among patients receiving trastuzumab plus chemotherapy as compared to chemotherapy alone: arthralgia (12.2% vs. 9.1%), nail changes (11.5% vs. 6.8%), dyspnea (2.4% vs. 0.2%), and diarrhea (2.2% vs. 0%). The majority of these events were Grade 2 in severity.

BCIRG006

Safety data from BCIRG006 reflect exposure to trastuzumab as part of an adjuvant treatment regimen from 2124 patients receiving at least one dose of study treatment [AC-TH: n = 1068; TCH: n = 1056]. The overall median treatment duration was 54 weeks in both the AC-TH and TCH arms. The median number of infusions was 26 in the AC-TH arm and 30 in the TCH arm, including weekly infusions during the chemotherapy phase and once every three weeks dosing in the monotherapy period [see Clinical Studies (14.1)]. In BCIRG006, the toxicity profile was similar to that reported in NSABP B31, NCCTG N9831, and HERA with the exception of a lower incidence of CHF in the TCH arm.

Metastatic Breast Cancer Studies

The safety of trastuzumab was evaluated in one randomized, open-label study (H0648g) of chemotherapy with (n = 235) or without (n = 234) intravenous trastuzumab in patients with metastatic breast cancer, and in one single-arm study (H0649g) in patients with metastatic breast cancer (n = 222) [see Clinical Studies (14.1)]. Patients received 4 mg/kg initial dose of trastuzumab followed by 2 mg/kg weekly. In H0648g, 58% of patients received trastuzumab for ≥ 6 months and 9% received trastuzumab for ≥ 12 months, respectively. In H0649g, 31% of patients received trastuzumab for ≥ 6 months and 16% received trastuzumab for ≥ 12 months, respectively.

Table 4 shows the adverse reactions (≥ 5%) in patients from H0648g and H0649g.

Table 4: Adverse Reactions [Data for trastuzumab single agent were from 4 studies, including 213 patients from H0649g.] (≥ 5%) in the Trastuzumab Arms in H0648g and H0649g
 | Trastuzumab n = 352; % | Trastuzumab + Paclitaxel n = 91; % | Paclitaxel n = 95; % | Trastuzumab + AC [Anthracycline (doxorubicin or epirubicin) and cyclophosphamide.] n = 143; % | AC n = 135; %
General
Pain | 47 | 61 | 62 | 57 | 42
Asthenia | 42 | 62 | 57 | 54 | 55
Fever | 36 | 49 | 23 | 56 | 34
Chills | 32 | 41 | 4 | 35 | 11
Headache | 26 | 36 | 28 | 44 | 31
Abdominal pain | 22 | 34 | 22 | 23 | 18
Back pain | 22 | 34 | 30 | 27 | 15
Infection | 20 | 47 | 27 | 47 | 31
Flu syndrome | 10 | 12 | 5 | 12 | 6
Accidental injury | 6 | 13 | 3 | 9 | 4
Allergic reaction | 3 | 8 | 2 | 4 | 2
Gastrointestinal
Nausea | 33 | 51 | 9 | 76 | 77
Diarrhea | 25 | 45 | 29 | 45 | 26
Vomiting | 23 | 37 | 28 | 53 | 49
Anorexia | 14 | 24 | 16 | 31 | 26
Nausea and vomiting | 8 | 14 | 11 | 18 | 9
Respiratory
Cough increased | 26 | 41 | 22 | 43 | 29
Dyspnea | 22 | 27 | 26 | 42 | 25
Rhinitis | 14 | 22 | 5 | 22 | 16
Pharyngitis | 12 | 22 | 14 | 30 | 18
Sinusitis | 9 | 21 | 7 | 13 | 6
Skin
Rash | 18 | 38 | 18 | 27 | 17
Herpes simplex | 2 | 12 | 3 | 7 | 9
Acne | 2 | 11 | 3 | 3 | < 1
Nervous
Insomnia | 14 | 25 | 13 | 29 | 15
Dizziness | 13 | 22 | 24 | 24 | 18
Paresthesia | 9 | 48 | 39 | 17 | 11
Depression | 6 | 12 | 13 | 20 | 12
Peripheral neuritis | 2 | 23 | 16 | 2 | 2
Neuropathy | 1 | 13 | 5 | 4 | 4
Metabolic
Peripheral edema | 10 | 22 | 20 | 20 | 17
Edema | 8 | 10 | 8 | 11 | 5
Cardiovascular
Congestive heart failure | 7 | 11 | 1 | 28 | 7
Tachycardia | 5 | 12 | 4 | 10 | 5
Musculoskeletal
Bone pain | 7 | 24 | 18 | 7 | 7
Arthralgia | 6 | 37 | 21 | 8 | 9
Urogenital
Urinary tract infection | 5 | 18 | 14 | 13 | 7
Blood and Lymphatic
Anemia | 4 | 14 | 9 | 36 | 26
Leukopenia | 3 | 24 | 17 | 52 | 34

Metastatic Gastric Cancer

The safety of trastuzumab was evaluated in patients with previously untreated for metastatic gastric or gastroesophageal junction adenocarcinoma in an open label, multi-center trial (ToGA) [see Clinical Studies (14.3)]. Patients were randomized (1:1) to receive trastuzumab in combination with cisplatin and a fluoropyrimidine (FC+H) (n=294) or chemotherapy alone (FC) (n=290). Patients in the trastuzumab plus chemotherapy arm received trastuzumab 8 mg/kg administered on Day 1 (prior to chemotherapy) followed by 6 mg/kg every 21 days until disease progression. Cisplatin was administered at 80 mg/m^2 on Day 1 and the fluoropyrimidine was administered as either capecitabine 1000 mg/m^2 orally twice a day on Days 1 to 14 or 5-fluorouracil 800 mg/m^2/day as a continuous intravenous infusion Days 1 through 5. Chemotherapy was administered for six 21-day cycles. Median duration of trastuzumab treatment was 21 weeks and the median number of trastuzumab infusions administered was eight.

Table 5: Adverse Reactions (All Grades ≥ 5% or Grade 3-4 ≥ 1% between Arms) in ToGA
Adverse Reactions | Trastuzumab + FC (N = 294) % |  | FC (N = 290) %
Adverse Reactions | All Grades | Grades 3-4 | All Grades | Grades 3-4
Investigations
Neutropenia | 78 | 34 | 73 | 29
Hypokalemia | 28 | 10 | 24 | 6
Anemia | 28 | 12 | 21 | 10
Thrombocytopenia | 16 | 5 | 11 | 3
Blood and Lymphatic System Disorders
Febrile Neutropenia | — | 5 | — | 3
Gastrointestinal Disorders
Diarrhea | 37 | 9 | 28 | 4
Stomatitis | 24 | 1 | 15 | 2
Dysphagia | 6 | 2 | 3 | < 1
General
Fatigue | 35 | 4 | 28 | 2
Fever | 18 | 1 | 12 | 0
Mucosal Inflammation | 13 | 2 | 6 | 1
Chills | 8 | < 1 | 0 | 0
Metabolism and Nutrition Disorders
Weight Decrease | 23 | 2 | 14 | 2
Infections and Infestations
Upper Respiratory Tract Infections | 19 | 0 | 10 | 0
Nasopharyngitis | 13 | 0 | 6 | 0
Renal and Urinary Disorders
Renal Failure and Impairment | 18 | 3 | 15 | 2
Nervous System Disorders
Dysgeusia | 10 | 0 | 5 | 0

The following subsections provide additional detail regarding adverse reactions observed in clinical trials of adjuvant breast cancer, metastatic breast cancer, metastatic gastric cancer, or post-marketing experience.

Cardiomyopathy

Serial measurement of cardiac function (LVEF) was obtained in clinical trials in the adjuvant treatment of breast cancer. In HERA, the median duration of follow-up was 12.6 months (12.4 months in the observation arm; 12.6 months in the 1-year trastuzumab arm); and in NSABP B31 and NCCTG N9831, 7.9 years in the AC-T arm, 8.3 years in the AC-TH arm. Following initiation of trastuzumab therapy, the incidence of new-onset dose-limiting myocardial dysfunction was higher among patients receiving trastuzumab and paclitaxel as compared to those receiving paclitaxel alone in NSABP B31 and NCCTG N9831, and in patients receiving one-year trastuzumab monotherapy compared to observation in HERA (see Table 6, Figures 1 and 2). The incidence of new-onset cardiac dysfunction, as measured by LVEF, remained similar when compared to the analysis performed at a median follow-up of 2.0 years in the AC-TH arm. This analysis showed evidence of reversibility of left ventricular dysfunction, with 64.5% of patients who experienced symptomatic CHF in the AC-TH group being asymptomatic at latest follow-up, and 90.3% having full or partial LVEF recovery.

Table 6: Myocardial Dysfunction (by LVEF) in NSABP B31, NCCTG N9831, HERA and BCIRG006 [For NSABP B31, NCCTG N9831 and HERA, events are counted from the beginning of trastuzumab treatment. For BCIRG006, events are counted from the date of randomization.]
Study and Arm | LVEF < 50% and Decrease from Baseline |  |  | LVEF Decrease
Study and Arm | LVEF; < 50% | ≥ 10% decrease | ≥ 16% decrease | < 20% and ≥ 10% | ≥ 20%
NSABP B31 & NCCTG N9831 [NSABP B31 and NCCTG N9831 regimens: doxorubicin and cyclophosphamide followed by paclitaxel (AC→T) or paclitaxel plus trastuzumab (AC→TH).] [Median duration of follow-up for NSABP B31 and NCCTG N9831 combined was 8.3 years in the AC→TH arm.]
AC→TH (n = 1856) | 23.1% (428) | 18.5% (344) | 11.2% (208) | 37.9% (703) | 8.9% (166)
AC→T (n = 1170) | 11.7% (137) | 7.0% (82) | 3.0% (35) | 22.1% (259) | 3.4% (40)
HERA [Median follow-up duration of 12.6 months in the one-year trastuzumab treatment arm.]
Trastuzumab (n = 1678) | 8.6% (144) | 7.0% (118) | 3.8% (64) | 22.4% (376) | 3.5% (59)
Observation (n = 1708) | 2.7% (46) | 2.0% (35) | 1.2% (20) | 11.9% (204) | 1.2% (21)
BCIRG006 [BCIRG006 regimens: doxorubicin and cyclophosphamide followed by docetaxel (AC→T) or docetaxel plus trastuzumab (AC→TH); docetaxel and carboplatin plus trastuzumab (TCH).]
TCH (n = 1056) | 8.5% (90) | 5.9% (62) | 3.3% (35) | 34.5% (364) | 6.3% (67)
AC→TH (n = 1068) | 17% (182) | 13.3% (142) | 9.8% (105) | 44.3% (473) | 13.2% (141)
AC→T (n = 1050) | 9.5% (100) | 6.6% (69) | 3.3% (35) | 34% (357) | 5.5% (58)

Figure 1

NSABP B31 and NCCTG N9831: Cumulative Incidence of Time to First LVEF Decline of ≥ 10 Percentage Points from Baseline and to Below 50% with Death as a Competing Risk Event

Time 0 is initiation of paclitaxel or trastuzumab + paclitaxel therapy.

Figure 2

HERA: Cumulative Incidence of Time to First LVEF Decline of ≥ 10 Percentage Points from Baseline and to Below 50% with Death as a Competing Risk Event

Time 0 is the date of randomization.

Figure 3

BCIRG006: Cumulative Incidence of Time to First LVEF Decline of ≥ 10 Percentage Points from Baseline and to Below 50% with Death as a Competing Risk Event

Time 0 is the date of randomization.

The incidence of congestive heart failure among patients in the metastatic breast cancer trials was classified for severity using the New York Heart Association classification system (I–IV, where IV is the most severe level of cardiac failure) (see Table 2). In the metastatic breast cancer trials, the probability of cardiac dysfunction was highest in patients who received trastuzumab concurrently with anthracyclines.

In ToGA, 5% of patients in the trastuzumab plus chemotherapy arm compared to 1.1% of patients in the chemotherapy alone arm had LVEF value below 50% with a ≥ 10% absolute decrease in LVEF from pretreatment values.

Infusion Reactions

During the first infusion with trastuzumab, the symptoms most commonly reported were chills and fever, occurring in approximately 40% of patients in clinical trials. Symptoms were treated with acetaminophen, diphenhydramine, and meperidine (with or without reduction in the rate of trastuzumab infusion); permanent discontinuation of trastuzumab for infusion reactions was required in < 1% of patients. Other signs and/or symptoms may include nausea, vomiting, pain (in some cases at tumor sites), rigors, headache, dizziness, dyspnea, hypotension, elevated blood pressure, rash, and asthenia. Infusion reactions occurred in 21% and 35% of patients, and were severe in 1.4% and 9% of patients, on second or subsequent trastuzumab infusions administered as monotherapy or in combination with chemotherapy, respectively. In the post-marketing setting, severe infusion reactions, including hypersensitivity, anaphylaxis, and angioedema have been reported.

Anemia

In randomized controlled clinical trials, the overall incidence of anemia (30% vs. 21% [H0648g]), of selected NCI-CTC Grade 2 to 5 anemia (12.3% vs. 6.7% [NSABP B31]), and of anemia requiring transfusions (0.1% vs. 0 patients [NCCTG N9831]) were increased in patients receiving trastuzumab and chemotherapy compared with those receiving chemotherapy alone. Following the administration of trastuzumab as a single agent (H0649g), the incidence of NCI-CTC Grade 3 anemia was < 1%. In ToGA (metastatic gastric cancer), on the trastuzumab containing arm as compared to the chemotherapy alone arm, the overall incidence of anemia was 28% compared to 21% and of NCI-CTC Grade 3/4 anemia was 12.2% compared to 10.3%.

Neutropenia

In randomized controlled clinical trials in the adjuvant setting, the incidence of selected NCI-CTC Grade 4 to 5 neutropenia (1.7% vs. 0.8% [NCCTG N9831]) and of selected Grade 2 to 5 neutropenia (6.4% vs. 4.3% [NSABP B31]) were increased in patients receiving trastuzumab and chemotherapy compared with those receiving chemotherapy alone. In a randomized, controlled trial in patients with metastatic breast cancer, the incidences of NCI-CTC Grade 3/4 neutropenia (32% vs. 22%) and of febrile neutropenia (23% vs. 17%) were also increased in patients randomized to trastuzumab in combination with myelosuppressive chemotherapy as compared to chemotherapy alone. In ToGA (metastatic gastric cancer) on the trastuzumab containing arm as compared to the chemotherapy alone arm, the incidence of NCI-CTC Grade 3/4 neutropenia was 36.8% compared to 28.9%; febrile neutropenia 5.1% compared to 2.8%.

Infection

The overall incidences of infection (46% vs. 30% [H0648g]), of selected NCI-CTC Grade 2 to 5 infection/febrile neutropenia (24.3% vs. 13.4% [NSABP B31]) and of selected Grade 3 to 5 infection/febrile neutropenia (2.9% vs. 1.4% [NCCTG N9831]) were higher in patients receiving trastuzumab and chemotherapy compared with those receiving chemotherapy alone. The most common site of infections in the adjuvant setting involved the upper respiratory tract, skin, and urinary tract.

In BCIRG006, the overall incidence of infection was higher with the addition of trastuzumab to AC-T but not to TCH [44% (AC-TH), 37% (TCH), 38% (AC-T)]. The incidences of NCI-CTC Grade 3 to 4 infection were similar [25% (AC-TH), 21% (TCH), 23% (AC-T)] across the three arms.

In a randomized, controlled trial in treatment of metastatic breast cancer, the reported incidence of febrile neutropenia was higher (23% vs. 17%) in patients receiving trastuzumab in combination with myelosuppressive chemotherapy as compared to chemotherapy alone.

Pulmonary Toxicity

Adjuvant Breast Cancer

Among women receiving adjuvant therapy for breast cancer, the incidence of selected NCI-CTC Grade 2 to 5 pulmonary toxicity (14.3% vs. 5.4% [NSABP B31]) and of selected NCI-CTC Grade 3 to 5 pulmonary toxicity and spontaneous reported Grade 2 dyspnea (3.4% vs. 0.9% [NCCTG N9831]) was higher in patients receiving trastuzumab and chemotherapy compared with chemotherapy alone. The most common pulmonary toxicity was dyspnea (NCI-CTC Grade 2 to 5: 11.8% vs. 4.6% [NSABP B31]; NCI-CTC Grade 2 to 5: 2.4% vs. 0.2% [NCCTG N9831]).

Pneumonitis/pulmonary infiltrates occurred in 0.7% of patients receiving trastuzumab compared with 0.3% of those receiving chemotherapy alone. Fatal respiratory failure occurred in 3 patients receiving trastuzumab, one as a component of multi-organ system failure, as compared to 1 patient receiving chemotherapy alone.

In HERA, there were 4 cases of interstitial pneumonitis in the one-year trastuzumab treatment arm compared to none in the observation arm at a median follow-up duration of 12.6 months.

Metastatic Breast Cancer

Among women receiving trastuzumab for treatment of metastatic breast cancer, the incidence of pulmonary toxicity was also increased. Pulmonary adverse events have been reported in the post-marketing experience as part of the symptom complex of infusion reactions. Pulmonary events include bronchospasm, hypoxia, dyspnea, pulmonary infiltrates, pleural effusions, non-cardiogenic pulmonary edema, and acute respiratory distress syndrome. For a detailed description, see Warnings and Precautions (5.4).

Thrombosis/Embolism

In 4 randomized, controlled clinical trials, the incidence of thrombotic adverse events was higher in patients receiving trastuzumab and chemotherapy compared to chemotherapy alone in three studies (2.6% vs. 1.5% [NSABP B31], 2.5% and 3.7% vs. 2.2% [BCIRG006] and 2.1% vs. 0% [H0648g]).

Diarrhea

Among women receiving adjuvant therapy for breast cancer, the incidence of NCI-CTC Grade 2 to 5 diarrhea (6.7% vs. 5.4% [NSABP B31]) and of NCI-CTC Grade 3 to 5 diarrhea (2.2% vs. 0% [NCCTG N9831]), and of Grade 1 to 4 diarrhea (7% vs. 1% [HERA; one-year trastuzumab treatment at 12.6 months median duration of follow-up]) were higher in patients receiving trastuzumab as compared to controls. In BCIRG006, the incidence of Grade 3 to 4 diarrhea was higher [5.7% AC-TH, 5.5% TCH vs. 3.0% AC-T] and of Grade 1 to 4 was higher [51% AC-TH, 63% TCH vs. 43% AC-T] among women receiving trastuzumab. Of patients receiving trastuzumab as a single agent for the treatment of metastatic breast cancer, 25% experienced diarrhea. An increased incidence of diarrhea was observed in patients receiving trastuzumab in combination with chemotherapy for treatment of metastatic breast cancer.

Renal Toxicity

In ToGA (metastatic gastric cancer) on the trastuzumab-containing arm as compared to the chemotherapy alone arm the incidence of renal impairment was 18% compared to 14.5%. Severe (Grade 3/4) renal failure was 2.7% on the trastuzumab-containing arm compared to 1.7% on the chemotherapy only arm. Treatment discontinuation for renal insufficiency/failure was 2% on the trastuzumab-containing arm and 0.3% on the chemotherapy only arm.

In the post-marketing setting, rare cases of nephrotic syndrome with pathologic evidence of glomerulopathy have been reported. The time to onset ranged from 4 months to approximately 18 months from initiation of trastuzumab therapy. Pathologic findings included membranous glomerulonephritis, focal glomerulosclerosis, and fibrillary glomerulonephritis. Complications included volume overload and congestive heart failure.

6.2 Post-Marketing Experience

The following adverse reactions have been identified during post-approval use of trastuzumab products. Because these reactions are reported voluntarily from a population of uncertain size, it is not always possible to reliably estimate their frequency or establish a causal relationship to drug exposure.

- Infusion reaction [see Warnings and Precautions (5.2)]
- Oligohydramnios or oligohydramnios sequence, including pulmonary hypoplasia, skeletal abnormalities, and neonatal death [see Warnings and Precautions (5.3)]
- Glomerulopathy [see Adverse Reactions (6.1)]
- Immune thrombocytopenia
- Tumor lysis syndrome (TLS): Cases of possible TLS have been reported in patients treated with trastuzumab products. Patients with significant tumor burden (e.g. bulky metastases) may be at a higher risk. Patients could present with hyperuricemia, hyperphosphatemia, and acute renal failure which may represent possible TLS. Providers should consider additional monitoring and/or treatment as clinically indicated.

7 DRUG INTERACTIONS

Anthracyclines

Patients who receive anthracycline after stopping trastuzumab products may be at increased risk of cardiac dysfunction because of trastuzumab products estimated long washout period [see Clinical Pharmacology (12.3)]. If possible, avoid anthracycline-based therapy for up to 7 months after stopping trastuzumab products. If anthracyclines are used, closely monitor the patient's cardiac function.

8 USE IN SPECIFIC POPULATIONS

8.1 Pregnancy

Risk Summary

Trastuzumab products can cause fetal harm when administered to a pregnant woman. In post-marketing reports and published literature, use of trastuzumab products during pregnancy resulted in cases of oligohydramnios and of oligohydramnios sequence, manifesting as pulmonary hypoplasia, skeletal abnormalities, and neonatal death (see Data). Apprise the patient of the potential risks to a fetus. There are clinical considerations if a trastuzumab product is used in a pregnant woman or if a patient becomes pregnant within 7 months following the last dose of a trastuzumab product (see Clinical Considerations).

The background risk of major birth defects and miscarriage for the indicated population is unknown. In the U.S. general population, the estimated background risk of major birth defects and miscarriage in clinically recognized pregnancies is 2% to 4% and 15% to 20%, respectively.

Clinical Considerations

Fetal/Neonatal Adverse Reactions

Monitor women who received TRAZIMERA during pregnancy or within 7 months prior to conception for oligohydramnios. If oligohydramnios occurs, perform fetal/neonatal testing that is appropriate for gestational age and consistent with community standards of care.

Data

Human Data

In post-marketing reports and published literature, use of trastuzumab products during pregnancy resulted in cases of oligohydramnios and of oligohydramnios sequence. Fetal manifestations included pulmonary hypoplasia, skeletal abnormalities and neonatal death. These case reports described oligohydramnios in pregnant women who received trastuzumab either alone or in combination with chemotherapy. In most reported cases, amniotic fluid index increased after trastuzumab was stopped. In reported cases where trastuzumab therapy was resumed after amniotic index improved, oligohydramnios recurred.

Animal Data

In studies where trastuzumab was administered to pregnant cynomolgus monkeys during the period of organogenesis at doses up to 25 mg/kg given twice weekly (up to 25 times the recommended weekly human dose of 2 mg/kg), trastuzumab crossed the placental barrier during the early (Gestation Days 20 to 50) and late (Gestation Days 120 to 150) phases of gestation. The resulting concentrations of trastuzumab in fetal serum and amniotic fluid were approximately 33% and 25%, respectively, of those present in the maternal serum but were not associated with adverse developmental effects.

8.2 Lactation

Risk Summary

There is no information regarding the presence of trastuzumab products in human milk, the effects on the breastfed infant, or the effects on milk production. Published data suggest human IgG is present in human milk but does not enter the neonatal and infant circulation in substantial amounts. Trastuzumab was present in the milk of lactating cynomolgus monkeys but not associated with neonatal toxicity (see Data). Consider the developmental and health benefits of breastfeeding along with the mother's clinical need for TRAZIMERA treatment and any potential adverse effects on the breastfed child from TRAZIMERA or from the underlying maternal condition. This consideration should also take into account the trastuzumab product wash out period of 7 months [see Clinical Pharmacology (12.3)].

Data

In lactating cynomolgus monkeys, trastuzumab was present in breast milk at about 0.3% of maternal serum concentrations after pre-(beginning Gestation Day 120) and post-partum (through Post-partum Day 28) doses of 25 mg/kg administered twice weekly (25 times the recommended weekly human dose of 2 mg/kg of trastuzumab products). Infant monkeys with detectable serum levels of trastuzumab did not exhibit any adverse effects on growth or development from birth to 1 month of age.

8.3 Females and Males of Reproductive Potential

Pregnancy Testing

Verify the pregnancy status of females of reproductive potential prior to the initiation of TRAZIMERA.

Contraception

Females

Trastuzumab products can cause embryo-fetal harm when administered during pregnancy. Advise females of reproductive potential to use effective contraception during treatment with TRAZIMERA and for 7 months following the last dose of TRAZIMERA [see Use in Specific Populations (8.1) and Clinical Pharmacology (12.3)].

8.4 Pediatric Use

The safety and effectiveness of TRAZIMERA in pediatric patients have not been established.

8.5 Geriatric Use

Trastuzumab has been administered to 386 patients who were 65 years of age or over (253 in the adjuvant treatment and 133 in metastatic breast cancer treatment settings). The risk of cardiac dysfunction was increased in geriatric patients as compared to younger patients in both those receiving treatment for metastatic disease in H0648g and H0649g, or adjuvant therapy in NSABP B31 and NCCTG N9831. Limitations in data collection and differences in study design of the 4 studies of trastuzumab in adjuvant treatment of breast cancer preclude a determination of whether the toxicity profile of trastuzumab in older patients is different from younger patients. The reported clinical experience is not adequate to determine whether the efficacy improvements (ORR, TTP, OS, DFS) of trastuzumab treatment in older patients is different from that observed in patients < 65 years of age for metastatic disease and adjuvant treatment.

In ToGA (metastatic gastric cancer), of the 294 patients treated with trastuzumab, 108 (37%) were 65 years of age or older, while 13 (4.4%) were 75 and over. No overall differences in safety or effectiveness were observed.

11 DESCRIPTION

Trastuzumab-qyyp is a humanized IgG1 kappa monoclonal antibody that selectively binds with high affinity to the extracellular domain of the human epidermal growth factor receptor 2 protein, HER2. Trastuzumab-qyyp is produced by recombinant DNA technology in a mammalian cell (Chinese Hamster Ovary) culture.

TRAZIMERA (trastuzumab-qyyp) for injection is a sterile, white, preservative-free lyophilized powder with a cake-like appearance, for intravenous administration.

Each multiple-dose vial of TRAZIMERA delivers 420 mg trastuzumab-qyyp, 7.9 mg L-histidine, 9.5 mg L-histidine HCl monohydrate, 1.7 mg polysorbate 20, and 386 mg sucrose. Reconstitution with 20 mL of the appropriate diluent (BWFI or SWFI) yields a solution containing 21 mg/mL trastuzumab-qyyp that delivers 20 mL (420 mg trastuzumab-qyyp), at a pH of approximately 6. If TRAZIMERA is reconstituted with SWFI without preservative, the reconstituted solution is considered single-dose.

Each single-dose vial of TRAZIMERA delivers 150 mg trastuzumab-qyyp, 2.8 mg L-histidine, 3.4 mg L-histidine HCl monohydrate, 0.6 mg polysorbate 20, and 138 mg sucrose. Reconstitution with 7.4 mL of SWFI yields a solution containing 21 mg/mL trastuzumab-qyyp that delivers 7.15 mL (150 mg trastuzumab-qyyp), at a pH of approximately 6.

12 CLINICAL PHARMACOLOGY

12.1 Mechanism of Action

The HER2 (or c-erbB2) proto-oncogene encodes a transmembrane receptor protein of 185 kDa, which is structurally related to the epidermal growth factor receptor. Trastuzumab products have been shown, in both in vitro assays and in animals, to inhibit the proliferation of human tumor cells that overexpress HER2.

Trastuzumab products are mediators of antibody-dependent cellular cytotoxicity (ADCC). In vitro, trastuzumab product-mediated ADCC has been shown to be preferentially exerted on HER2 overexpressing cancer cells compared with cancer cells that do not overexpress HER2.

12.2 Pharmacodynamics

Trastuzumab product exposure-response relationships and the time course of pharmacodynamic responses are not fully characterized.

Cardiac Electrophysiology

The effects of trastuzumab on electrocardiographic (ECG) endpoints, including QTc interval duration, were evaluated in patients with HER2 positive solid tumors. Trastuzumab had no clinically relevant effect on the QTc interval duration and there was no apparent relationship between serum trastuzumab concentrations and change in QTcF interval duration in patients with HER2 positive solid tumors.

12.3 Pharmacokinetics

The pharmacokinetics of trastuzumab were evaluated in a pooled population pharmacokinetic (PK) model analysis of 1,582 subjects with primarily breast cancer and metastatic gastric cancer (MGC) receiving intravenous trastuzumab. Total trastuzumab clearance increases with decreasing concentrations due to parallel linear and non-linear elimination pathways.

Although the average trastuzumab exposure was higher following the first cycle in breast cancer patients receiving the once every three weeks schedule compared to the weekly schedule of trastuzumab, the average steady-state exposure was essentially the same at both dosages. The average trastuzumab exposure following the first cycle and at steady state as well as the time to steady state was higher in breast cancer patients compared to MGC patients at the same dosage; however, the reason for this exposure difference is unknown. Additional predicted trastuzumab exposure and PK parameters following the first trastuzumab cycle and at steady state exposure are described in Tables 7 and 8, respectively.

Population PK based simulations indicate that following discontinuation of trastuzumab, concentrations in at least 95% of breast cancer patients and MGC patients will decrease to approximately 3% of the population predicted steady-state trough serum concentration (approximately 97% washout) by 7 months [see Warnings and Precautions (5.1) and Use in Specific Populations (8.1, 8.3)].

Table 7: Population Predicted Cycle 1 PK Exposures (Median with 5th to 95th Percentiles) in Breast Cancer and MGC Patients
Schedule | Primary tumor type | N | Cmin (µg/mL) | Cmax (µg/mL) | AUC0-21 days (µg.day/mL)
8 mg/kg + 6 mg/kg q3w | Breast cancer | 1195 | 29.4 (5.8 to 59.5) | 178 (117 to 291) | 1373 (736 to 2245)
8 mg/kg + 6 mg/kg q3w | MGC | 274 | 23.1 (6.1 to 50.3) | 132 (84.2 to 225) | 1109 (588 to 1938)
4 mg/kg + 2 mg/kg qw | Breast cancer | 1195 | 37.7 (12.3 to 70.9) | 88.3 (58 to 144) | 1066 (586 to 1754)

Table 8: Population Predicted Steady State PK Exposures (Median with 5th to 95th Percentiles) in Breast Cancer and MGC Patients
Schedule | Primary tumor type | N | Cmin,ss [Steady-state trough serum concentration of trastuzumab.] (µg/mL) | Cmax,ss [Maximum steady-state serum concentration of trastuzumab.] (µg/mL) | AUCss, 0-21 days (µg.day/mL) | Time to steady-state (week) | Total CL range at steady-state (L/day)
8 mg/kg + 6 mg/kg q3w | Breast cancer | 1195 | 47.4 (5 to 115) | 179 (107 to 309) | 1794 (673 to 3618) | 12 | 0.173 to 0.283
8 mg/kg + 6 mg/kg q3w | MGC | 274 | 32.9 (6.1 to 88.9) | 131 (72.5 to 251) | 1338 (557 to 2875) | 9 | 0.189 to 0.337
4 mg/kg + 2 mg/kg qw | Breast cancer | 1195 | 66.1 (14.9 to 142) | 109 (51.0 to 209) | 1765 (647 to 3578) | 12 | 0.201 to 0.244

Specific Populations

Based on a population pharmacokinetic analysis, no clinically significant differences were observed in the pharmacokinetics of trastuzumab based on age (< 65 (n = 1294); ≥ 65 (n = 288)), race (Asian (n = 264); non-Asian (n = 1324)) and renal impairment (mild (creatinine clearance [CLcr] 60 to 90 mL/min) (n = 636) or moderate (CLcr 30 to 60 mL/min) (n = 133)). The pharmacokinetics of trastuzumab products in patients with severe renal impairment, end-stage renal disease with or without hemodialysis, or hepatic impairment are unknown.

Drug Interaction Studies

There have been no formal drug interaction studies performed with trastuzumab products in humans. Clinically significant interactions between trastuzumab and concomitant medications used in clinical trials have not been observed.

Paclitaxel and Doxorubicin

Concentrations of paclitaxel and doxorubicin and their major metabolites (i.e., 6-α hydroxyl-paclitaxel [POH], and doxorubicinol [DOL], respectively) were not altered in the presence of trastuzumab when used as combination therapy in clinical trials. Trastuzumab concentrations were not altered as part of this combination therapy.

Docetaxel and Carboplatin

When trastuzumab was administered in combination with docetaxel or carboplatin, neither the plasma concentrations of docetaxel or carboplatin nor the plasma concentrations of trastuzumab were altered.

Cisplatin and Capecitabine

In a drug interaction substudy conducted in patients in ToGA, the pharmacokinetics of cisplatin, capecitabine and their metabolites were not altered when administered in combination with trastuzumab.

12.6 Immunogenicity

The observed incidence of anti-drug antibodies is highly dependent on the sensitivity and specificity of the assay. Differences in assay methods preclude meaningful comparisons of the incidence of anti-drug antibodies in the studies described below with the incidence of anti-drug antibodies in other studies, including those of trastuzumab or of other trastuzumab products.

Among 903 women with metastatic breast cancer, human anti-human antibody (HAHA) to trastuzumab was detected in one patient using an enzyme-linked immunosorbent assay (ELISA). This patient did not experience an allergic reaction. Samples for assessment of HAHA were not collected in studies of adjuvant breast cancer.

The clinical relevance of the development of anti-trastuzumab antibodies after treatment with trastuzumab is not known.

13 NONCLINICAL TOXICOLOGY

13.1 Carcinogenesis, Mutagenesis, Impairment of Fertility

Trastuzumab products have not been tested for carcinogenic potential.

No evidence of mutagenic activity was observed when trastuzumab was tested in the standard Ames bacterial and human peripheral blood lymphocyte mutagenicity assays at concentrations of up to 5000 mcg/mL. In an in vivo micronucleus assay, no evidence of chromosomal damage to mouse bone marrow cells was observed following bolus intravenous doses of up to 118 mg/kg of trastuzumab.

A fertility study was conducted in female cynomolgus monkeys at doses up to 25 times the weekly recommended human dose of 2 mg/kg of trastuzumab and has revealed no evidence of impaired fertility, as measured by menstrual cycle duration and female sex hormone levels.

14 CLINICAL STUDIES

14.1 Adjuvant Breast Cancer

The safety and efficacy of trastuzumab in women receiving adjuvant chemotherapy for HER2 overexpressing breast cancer were evaluated in an integrated analysis of two randomized, open-label, clinical trials (NSABP B31 and NCCTG N9831) with a total of 4063 women at the protocol-specified final overall survival analysis, a third randomized, open-label, clinical trial (HERA) with a total of 3386 women at definitive Disease-Free Survival analysis for one-year trastuzumab treatment versus observation, and a fourth randomized, open-label clinical trial with a total of 3222 patients (BCIRG006).

NSABP B31 and NCCTG N9831

In NSABP B31 and NCCTG N9831, breast tumor specimens were required to show HER2 overexpression (3+ by IHC) or gene amplification (by FISH). HER2 testing was verified by a central laboratory prior to randomization (NCCTG N9831) or was required to be performed at a reference laboratory (NSABP B31). Patients with a history of active cardiac disease based on symptoms, abnormal electrocardiographic, radiologic, or left ventricular ejection fraction findings or uncontrolled hypertension (diastolic > 100 mm Hg or systolic > 200 mm Hg) were not eligible.

Patients were randomized (1:1) to receive doxorubicin and cyclophosphamide followed by paclitaxel (AC→paclitaxel) alone or paclitaxel plus trastuzumab (AC→paclitaxel + trastuzumab). In both trials, patients received four 21-day cycles of doxorubicin 60 mg/m^2 and cyclophosphamide 600 mg/m^2. Paclitaxel was administered either weekly (80 mg/m^2) or every 3 weeks (175 mg/m^2) for a total of 12 weeks in NSABP B31; paclitaxel was administered only by the weekly schedule in NCCTG N9831. Trastuzumab was administered at 4 mg/kg on the day of initiation of paclitaxel and then at a dose of 2 mg/kg weekly for a total of 52 weeks. Trastuzumab treatment was permanently discontinued in patients who developed congestive heart failure, or persistent/recurrent LVEF decline [see Dosage and Administration (2.5)]. Radiation therapy, if administered, was initiated after the completion of chemotherapy. Patients with ER+ and/or PR+ tumors received hormonal therapy. The major efficacy outcome measure of the combined efficacy analysis was Disease-Free Survival (DFS), defined as the time from randomization to recurrence, occurrence of contralateral breast cancer, other second primary cancer, or death. An additional efficacy outcome measure was overall survival (OS).

A total of 3752 patients were included in the joint efficacy analysis of DFS following a median follow-up of 2.0 years in the AC→paclitaxel + trastuzumab arm. The pre-planned final OS analysis from the joint analysis included 4063 patients and was performed when 707 deaths had occurred after a median follow-up of 8.3 years in the AC→paclitaxel + trastuzumab arm. The data from both arms in NSABP B31 and two of the three study arms in NCCTG N9831 were pooled for efficacy analyses.

The patients included in the DFS analysis had a median age of 49 years (range, 22 to 80 years; 6% > 65 years), 84% were White, 7% Black, 4% Hispanic, and 4% Asian/Pacific Islander. Disease characteristics included 90% infiltrating ductal histology, 38% T1, 91% nodal involvement, 27% intermediate and 66% high grade pathology, and 53% ER+ and/or PR+ tumors.

HERA

In HERA, breast tumor specimens were required to show HER2 overexpression (3+ by IHC) or gene amplification (by FISH) as determined at a central laboratory. Patients with node-negative disease were required to have ≥ T1c primary tumor. Patients with a history of congestive heart failure or LVEF < 55%, uncontrolled arrhythmias, angina requiring medication, clinically significant valvular heart disease, evidence of transmural infarction on ECG, poorly controlled hypertension (systolic > 180 mm Hg or diastolic > 100 mm Hg) were not eligible.

Patients were randomized (1:1:1) upon completion of definitive surgery, and at least four cycles of chemotherapy to receive no additional treatment, or one year of trastuzumab treatment or two years of trastuzumab treatment. Patients undergoing a lumpectomy had also completed standard radiotherapy. Patients with ER+ and/or PgR+ disease received systemic adjuvant hormonal therapy at investigator discretion. Trastuzumab was administered with an initial dose of 8 mg/kg followed by subsequent doses of 6 mg/kg once every three weeks. The major efficacy outcome measure was Disease-Free Survival (DFS), defined as in NSABP B31 and NCCTG N9831.

HERA was designed to compare one and two years of once every three weeks trastuzumab treatment versus observation in patients with HER2 positive EBC following surgery, established chemotherapy and radiotherapy (if applicable). A protocol-specified interim efficacy analysis comparing one-year trastuzumab treatment to observation was performed at a median follow-up duration of 12.6 months in the trastuzumab arm.

Among the 3386 patients randomized to the observation (n = 1693) and trastuzumab one-year (n = 1693) treatment arms, the median age was 49 years (range 21 to 80), 83% were White, and 13% were Asian. Disease characteristics: 94% infiltrating ductal carcinoma, 50% ER+ and/or PgR+, 57% node positive, 32% node negative, and in 11% of patients, nodal status was not assessable due to prior neo-adjuvant chemotherapy. Ninety-six percent (1055/1098) of patients with node-negative disease had high-risk features: among the 1098 patients with node-negative disease, 49% (543) were ER− and PgR−, and 47% (512) were ER and/or PgR+ and had at least one of the following high-risk features: pathological tumor size greater than 2 cm, Grade 2 to 3, or age < 35 years. Prior to randomization, 94% of patients had received anthracycline-based chemotherapy regimens.

After the DFS results comparing observation to one-year trastuzumab treatment were disclosed, a prospectively planned analysis that included comparison of one year versus two years of trastuzumab treatment at a median follow-up duration of 8 years was performed. Based on this analysis, extending trastuzumab treatment for a duration of two years did not show additional benefit over treatment for one year [Hazard Ratios of two-years trastuzumab versus one-year trastuzumab treatment in the intent to treat (ITT) population for Disease-Free Survival (DFS) = 0.99 (95% CI: 0.87, 1.13), p-value = 0.90 and Overall Survival (OS) = 0.98 (0.83, 1.15); p-value = 0.78].

BCIRG006

In BCIRG006, breast tumor specimens were required to show HER2 gene amplification (FISH+ only) as determined at a central laboratory. Patients were required to have either node-positive disease, or node-negative disease with at least one of the following high-risk features: ER/PR-negative, tumor size > 2 cm, age < 35 years, or histologic and/or nuclear Grade 2 or 3. Patients with a history of CHF, myocardial infarction, Grade 3 or 4 cardiac arrhythmia, angina requiring medication, clinically significant valvular heart disease, poorly controlled hypertension (diastolic > 100 mm Hg), any T4 or N2 or known N3 or M1 breast cancer were not eligible.

Patients were randomized (1:1:1) to receive doxorubicin and cyclophosphamide followed by docetaxel (AC-T), doxorubicin and cyclophosphamide followed by docetaxel plus trastuzumab (AC-TH), or docetaxel and carboplatin plus trastuzumab (TCH). In both the AC-T and AC-TH arms, doxorubicin 60 mg/m^2 and cyclophosphamide 600 mg/m^2 were administered every 3 weeks for four cycles; docetaxel 100 mg/m^2 was administered every 3 weeks for four cycles. In the TCH arm, docetaxel 75 mg/m^2 and carboplatin (at a target AUC of 6 mg/mL/min as a 30- to 60-minute infusion) were administered every 3 weeks for six cycles. Trastuzumab was administered weekly (initial dose of 4 mg/kg followed by weekly dose of 2 mg/kg) concurrently with either T or TC, and then every 3 weeks (6 mg/kg) as monotherapy for a total of 52 weeks. Radiation therapy, if administered, was initiated after completion of chemotherapy. Patients with ER+ and/or PR+ tumors received hormonal therapy. Disease-Free Survival (DFS) was the major efficacy outcome measure.

Among 3222 patients, the median age was 49 (range 22 to 74 years; 6% ≥ 65 years). Disease characteristics included 54% ER+ and/or PR+ and 71% node positive. Prior to randomization, all patients underwent primary surgery for breast cancer.

The results for DFS for the integrated analysis of NSABP B31 and NCCTG N9831, HERA, and BCIRG006 and OS results for the integrated analysis of NSABP B31 and NCCTG N9831, and HERA are presented in Table 9. For NSABP B31 and NCCTG N9831, the duration of DFS following a median follow-up of 2.0 years in the AC→TH arm is presented in Figure 4, and the duration of OS after a median follow-up of 8.3 years in the AC→TH arm is presented in Figure 5. The duration of DFS for BCIRG006 is presented in Figure 6. For NSABP B31 and NCCTG N9831, the OS hazard ratio was 0.64 (95% CI: 0.55, 0.74). At 8.3 years of median follow-up [AC→TH], the survival rate was estimated to be 86.9% in the AC→TH arm and 79.4% in the AC→T arm. The final OS analysis results from NSABP B31 and NCCTG N9831 indicate that OS benefit by age, hormone receptor status, number of positive lymph nodes, tumor size and grade, and surgery/radiation therapy was consistent with the treatment effect in the overall population. In patients ≤ 50 years of age (n = 2197), the OS hazard ratio was 0.65 (95% CI: 0.52, 0.81) and in patients > 50 years of age (n = 1866), the OS hazard ratio was 0.63 (95% CI: 0.51, 0.78). In the subgroup of patients with hormone receptor-positive disease (ER-positive and/or PR-positive) (n = 2223), the hazard ratio for OS was 0.63 (95% CI: 0.51, 0.78). In the subgroup of patients with hormone receptor‑negative disease (ER-negative and PR-negative) (n = 1830), the hazard ratio for OS was 0.64 (95% CI: 0.52, 0.80). In the subgroup of patients with tumor size ≤ 2 cm (n = 1604), the hazard ratio for OS was 0.52 (95% CI: 0.39, 0.71). In the subgroup of patients with tumor size > 2 cm (n = 2448), the hazard ratio for OS was 0.67 (95% CI: 0.56, 0.80).

Table 9: Efficacy Results from Adjuvant Treatment of Breast Cancer (NSABP B31 and NCCTG N9831, HERA, and BCIRG006)
 | DFS events | DFS Hazard ratio (95% CI) p-value | Deaths (OS events) | OS Hazard ratio p-value
NSABP B31 and NCCTG N9831 [NSABP B31 and NCCTG N9831 regimens: doxorubicin and cyclophosphamide followed by paclitaxel (AC→T) or paclitaxel plus trastuzumab (AC→TH).]
AC→TH (n = 1872) [Efficacy evaluable population, for the primary DFS analysis, following a median follow-up of 2.0 years in the AC→TH arm.] (n = 2031) [Efficacy evaluable population, for the final OS analysis, following 707 deaths (8.3 years of median follow-up in the AC→TH arm).] | 133 | 0.48 [Hazard ratio estimated by Cox regression stratified by clinical trial, intended paclitaxel schedule, number of positive nodes, and hormone receptor status.] (0.39, 0.59) p< 0.0001 [stratified log-rank test.] | 289 | 0.64 (0.55, 0.74) p< 0.0001
AC→T (n = 1880) (n = 2032) | 261 |  | 418
HERA [At definitive DFS analysis with median duration of follow-up of 12.6 months in the one-year trastuzumab treatment arm.]
Chemo→ Trastuzumab (n = 1693) | 127 | 0.54 (0.44, 0.67) p< 0.0001 [log-rank test.] | 31 | 0.75 p = NS [NS = non-significant.]
Chemo→ Observation (n = 1693) | 219 |  | 40
BCIRG006 [BCIRG006 regimens: doxorubicin and cyclophosphamide followed by docetaxel (AC→T) or docetaxel plus trastuzumab (AC→TH); docetaxel and carboplatin plus trastuzumab (TCH).]
TCH (n = 1075) | 134 | 0.67 (0.54 – 0.84) p=0.0006 [A two-sided alpha level of 0.025 for each comparison.] | 56
AC→TH (n = 1074) | 121 | 0.60 (0.48 – 0.76) p< 0.0001 | 49
AC→T (n = 1073) | 180 |  | 80
CI = confidence interval.

Figure 4

Duration of Disease-Free Survival in Patients with Adjuvant Treatment of Breast Cancer (NSABP B31 and NCCTG N9831)

Figure 5

Overall Survival in Patients with Adjuvant Treatment of Breast Cancer (NSABP B31 and NCCTG N9831)

Figure 6

Disease-Free Survival in Patients with Adjuvant Treatment of Breast Cancer (BCIRG006)

Exploratory analyses of DFS as a function of HER2 overexpression or gene amplification were conducted for patients in NCCTG N9831 and HERA, where central laboratory testing data were available. The results are shown in Table 10. The number of events in NCCTG N9831 was small with the exception of the IHC 3+/FISH+ subgroup, which constituted 81% of those with data. Definitive conclusions cannot be drawn regarding efficacy within other subgroups due to the small number of events. The number of events in HERA was adequate to demonstrate significant effects on DFS in the IHC 3+/FISH unknown and the FISH+/IHC unknown subgroups.

Table 10: DFS in NCCTG N9831 and HERA for Patients with HER2 Overexpression or Amplification
 | NCCTG N9831 |  | HERA [Median follow-up duration of 12.6 months in the one-year trastuzumab treatment arm.]
HER2 Assay Result [IHC by HercepTest, FISH by PathVysion (HER2/CEP17 ratio ≥ 2.0) as performed at a central laboratory.] | Number of Patients | Hazard Ratio DFS (95% CI) | Number of Patients | Hazard Ratio DFS (95% CI)
IHC 3+
FISH (+) | 1170 | 0.42; (0.27, 0.64) | 91 | 0.56; (0.13, 2.50)
FISH (−) | 51 | 0.71; (0.04, 11.79) | 8 | —
FISH Unknown | 51 | 0.69; (0.09, 5.14) | 2258 | 0.53; (0.41, 0.69)
IHC < 3+ /; FISH (+) | 174 | 1.01; (0.18, 5.65) | 299 [All cases in this category in HERA were IHC 2+.] | 0.53; (0.20, 1.42)
IHC unknown / FISH (+) | — | — | 724 | 0.59; (0.38, 0.93)

14.2 Metastatic Breast Cancer

The safety and efficacy of trastuzumab in treatment of women with metastatic breast cancer were studied in a randomized, controlled clinical trial in combination with chemotherapy (H0648g, n = 469 patients) and an open-label single agent clinical trial (H0649g, n = 222 patients). Both trials studied patients with metastatic breast cancer whose tumors overexpress the HER2 protein. Patients were eligible if they had 2 or 3 levels of overexpression (based on a 0 to 3 scale) by immunohistochemical assessment of tumor tissue performed by a central testing lab.

Previously Untreated Metastatic Breast Cancer (H0648g)

H0648g was a multicenter, randomized, open-label clinical trial conducted in 469 women with metastatic breast cancer who had not been previously treated with chemotherapy for metastatic disease. Tumor specimens were tested by IHC (Clinical Trial Assay, CTA) and scored as 0, 1+, 2+, or 3+, with 3+ indicating the strongest positivity. Only patients with 2+ or 3+ positive tumors were eligible (about 33% of those screened). Patients were randomized to receive chemotherapy alone or in combination with trastuzumab given intravenously as a 4 mg/kg loading dose followed by weekly doses of trastuzumab at 2 mg/kg. For those who had received prior anthracycline therapy in the adjuvant setting, chemotherapy consisted of paclitaxel (175 mg/m^2 over 3 hours every 21 days for at least six cycles); for all other patients, chemotherapy consisted of anthracycline plus cyclophosphamide (AC: doxorubicin 60 mg/m^2 or epirubicin 75 mg/m^2 plus 600 mg/m^2 cyclophosphamide every 21 days for six cycles). Sixty-five percent of patients randomized to receive chemotherapy alone in this study received trastuzumab at the time of disease progression as part of a separate extension study.

Based upon the determination by an independent Response Evaluation Committee, the patients randomized to trastuzumab and chemotherapy experienced a significantly longer median time to disease progression (TTP), a higher overall response rate (ORR), and a longer median duration of response (DoR) as compared with patients randomized to chemotherapy alone. Patients randomized to trastuzumab and chemotherapy also had a longer median overall survival (OS) (see Table 11). These treatment effects were observed both in patients who received trastuzumab plus paclitaxel and in those who received trastuzumab plus AC; however, the magnitude of the effects was greater in the paclitaxel subgroup.

Table 10: H0648g: Efficacy Results in First-Line Treatment for Metastatic Breast Cancer
 | Combined Results |  | Paclitaxel Subgroup |  | AC [AC = Anthracycline (doxorubicin or epirubicin) and cyclophosphamide.] Subgroup
 | Trastuzumab + All Chemotherapy (n = 235) | All Chemotherapy (n = 234) | Trastuzumab + Paclitaxel (n = 92) | Paclitaxel (n = 96) | Trastuzumab + AC (n = 143) | AC (n = 138)
Time to Disease Progression (TTP)
Median (months) [Assessed by an independent Response Evaluation Committee.] [Kaplan-Meier Estimate.] | 7.2 | 4.5 | 6.7 | 2.5 | 7.6 | 5.7
95% CI | 7, 8 | 4, 5 | 5, 10 | 2, 4 | 7, 9 | 5, 7
p-value [log-rank test.] | < 0.001 |  | < 0.001 |  | 0.002
Overall Response Rate (ORR)
Events (n) | 45 | 29 | 38 | 15 | 50 | 38
95% CI | 39, 51 | 23, 35 | 28, 48 | 8, 22 | 42, 58 | 30, 46
p-value [χ2-test.] | < 0.0001 |  | < 0.0001 |  | 0.10
Duration of Response (DoR)
Median (months) | 8.3 | 5.8 | 8.3 | 4.3 | 8.4 | 6.4
25%, 75% Quartile | 6, 15 | 4, 8 | 5, 11 | 4, 7 | 6, 15 | 4, 8
Overall Survival (OS)
Median (months) | 25.1 | 20.3 | 22.1 | 18.4 | 26.8 | 21.4
95% CI | 22, 30 | 17, 24 | 17, 29 | 13, 24 | 23, 33 | 18, 27
p-value | 0.05 |  | 0.17 |  | 0.16

Data from H0648g suggest that the beneficial treatment effects were largely limited to patients with the highest level of HER2 protein overexpression (3+) (see Table 12).

Table 11: Treatment Effects in H0648g as a Function of HER2 Overexpression or Amplification
HER2 Assay Result | Number of Patients (N) | Relative Risk [The relative risk represents the risk of progression or death in the trastuzumab plus chemotherapy arm versus the chemotherapy arm.] for Time to Disease Progression (95% CI) | Relative Risk for Mortality (95% CI)
CTA 2+ or 3+ | 469 | 0.49 (0.40, 0.61) | 0.80 (0.64, 1.00)
FISH (+) [FISH testing results were available for 451 of the 469 patients enrolled on study.] | 325 | 0.44 (0.34, 0.57) | 0.70 (0.53, 0.91)
FISH (−) | 126 | 0.62 (0.42, 0.94) | 1.06 (0.70, 1.63)
CTA 2+ | 120 | 0.76 (0.50, 1.15) | 1.26 (0.82, 1.94)
FISH (+) | 32 | 0.54 (0.21, 1.35) | 1.31 (0.53, 3.27)
FISH (–) | 83 | 0.77 (0.48, 1.25) | 1.11 (0.68, 1.82)
CTA 3+ | 349 | 0.42 (0.33, 0.54) | 0.70 (0.51, 0.90)
FISH (+) | 293 | 0.42 (0.32, 0.55) | 0.67 (0.51, 0.89)
FISH (–) | 43 | 0.43 (0.20, 0.94) | 0.88 (0.39, 1.98)

Previously Treated Metastatic Breast Cancer (H0649g)

Trastuzumab was studied as a single agent in a multicenter, open-label, single-arm clinical trial (H0649g) in patients with HER2 overexpressing metastatic breast cancer who had relapsed following one or two prior chemotherapy regimens for metastatic disease. Of 222 patients enrolled, 66% had received prior adjuvant chemotherapy, 68% had received two prior chemotherapy regimens for metastatic disease, and 25% had received prior myeloablative treatment with hematopoietic rescue. Patients were treated with a loading dose of 4 mg/kg IV followed by weekly doses of trastuzumab at 2 mg/kg IV.

The ORR (complete response + partial response), as determined by an independent Response Evaluation Committee, was 14%, with a 2% complete response rate and a 12% partial response rate. Complete responses were observed only in patients with disease limited to skin and lymph nodes. The overall response rate in patients whose tumors tested as CTA 3+ was 18% while in those that tested as CTA 2+, it was 6%.

14.3 Metastatic Gastric Cancer

The safety and efficacy of trastuzumab in combination with cisplatin and a fluoropyrimidine (capecitabine or 5-fluorouracil) were studied in patients previously untreated for metastatic gastric or gastroesophageal junction adenocarcinoma (ToGA). In this open-label, multi-center trial, 594 patients were randomized 1:1 to trastuzumab in combination with cisplatin and a fluoropyrimidine (FC+H) or chemotherapy alone (FC). Randomization was stratified by extent of disease (metastatic vs. locally advanced), primary site (gastric vs. gastroesophageal junction), tumor measurability (yes vs. no), ECOG performance status (0,1 vs. 2), and fluoropyrimidine (capecitabine vs. 5-fluorouracil). All patients were either HER2 gene amplified (FISH+) or HER2 overexpressing (IHC 3+). Patients were also required to have adequate cardiac function (e.g., LVEF > 50%).

On the trastuzumab-containing arm, trastuzumab was administered as an IV infusion at an initial dose of 8 mg/kg followed by 6 mg/kg every 3 weeks until disease progression. On both study arms cisplatin was administered at a dose of 80 mg/m^2 Day 1 every 3 weeks for 6 cycles as a 2 hour IV infusion. On both study arms, capecitabine was administered at 1000 mg/m^2 dose orally twice daily (total daily dose 2000 mg/m^2) for 14 days of each 21 day cycle for 6 cycles. Alternatively, continuous intravenous infusion (CIV) 5-fluorouracil was administered at a dose of 800 mg/m^2/day from Day 1 through Day 5 every three weeks for 6 cycles.

The median age of the study population was 60 years (range: 21 to 83); 76% were male; 53% were Asian, 38% Caucasian, 5% Hispanic, 5% other racial/ethnic groups; 91% had ECOG PS of 0 or 1; 82% had primary gastric cancer and 18% had primary gastroesophageal adenocarcinoma. Of these patients, 23% had undergone prior gastrectomy, 7% had received prior neoadjuvant and/or adjuvant therapy, and 2% had received prior radiotherapy.

The main outcome measure of ToGA was overall survival (OS), analyzed by the unstratified log-rank test. The final OS analysis based on 351 deaths was statistically significant (nominal significance level of 0.0193). An updated OS analysis was conducted at one year after the final analysis. The efficacy results of both the final and the updated analyses are summarized in Table 13 and Figure 7.

Table 12: Overall Survival in ToGA (ITT Population)
 | FC [FC = capecitabine vs. 5-fluorouracil.] + Trastuzumab Arm N = 298 | FC Arm N = 296
Overall Survival (interim analysis)
N (%) | 167 (56.0%) | 184 (62.2%)
Median (months) | 13.5 | 11.0
95% CI | (11.7, 15.7) | (9.4, 12.5)
Hazard Ratio | 0.73
95% CI | (0.60, 0.91)
p-value [Two sided p-value comparing with the nominal significance level of 0.0193.] | 0.0038
Overall Survival (updated)
N (%) | 221 (74.2%) | 227 (76.7%)
Median (months) | 13.1 | 11.7
95% CI | (11.9, 15.1) | (10.3, 13.0)
Hazard Ratio | 0.80
95% CI | (0.67, 0.97)

Figure 7

Updated Overall Survival in Patients with Metastatic Gastric Cancer (ToGA)

An exploratory analysis of OS in patients based on HER2 gene amplification (FISH) and protein overexpression (IHC) testing is summarized in Table 14.

Table 13: Exploratory Analyses by HER2 Status Using Updated Overall Survival Results
 | FC (N = 296) [Two patients on the FC arm who were FISH+ but IHC status unknown were excluded from the exploratory subgroup analyses.] | FC + H (N = 298) [Five patients on the trastuzumab-containing arm who were FISH+, but IHC status unknown were excluded from the exploratory subgroup analyses.]
FISH+ / IHC 0, 1+ subgroup (N=133)
No. Deaths / n (%) | 57/71 (80%) | 56/62 (90%)
Median OS Duration (mos.) | 8.8 | 8.3
95% CI (mos.) | (6.4, 11.7) | (6.2, 10.7)
Hazard ratio (95% CI) | 1.33 (0.92, 1.92)
FISH+ / IHC2+ subgroup (N=160)
No. Deaths / n (%) | 65/80 (81%) | 64/80 (80%)
Median OS Duration (mos.) | 10.8 | 12.3
95% CI (mos.) | (6.8, 12.8) | (9.5, 15.7)
Hazard ratio (95% CI) | 0.78 (0.55, 1.10)
FISH+ or FISH- / IHC3+ [Includes 6 patients on chemotherapy arm, 10 patients on trastuzumab arm with FISH-, IHC3+ and 8 patients on chemotherapy arm, 8 patients on trastuzumab arm with FISH status unknown, IHC 3+.] subgroup (N=294)
No. Deaths / n (%) | 104/143 (73%) | 96/151 (64%)
Median OS Duration (mos.) | 13.2 | 18.0
95% CI (mos.) | (11.5, 15.2) | (15.5, 21.2)
Hazard ratio (95% CI) | 0.66 (0.50, 0.87)

16 HOW SUPPLIED/STORAGE AND HANDLING

420 mg Multiple-dose vial

TRAZIMERA (trastuzumab-qyyp) for injection 420 mg/vial is supplied in a multiple-dose vial as a sterile, white lyophilized powder. Each carton contains one multiple-dose vial of TRAZIMERA and one vial (20 mL) of Bacteriostatic Water for Injection (BWFI) containing 1.1% benzyl alcohol as a preservative.

NDC 0069-0305-01.

150 mg Single-dose vial

TRAZIMERA (trastuzumab-qyyp) for injection 150 mg/vial is supplied in a single-dose vial as a sterile, white lyophilized powder. Each carton contains one single-dose vial of TRAZIMERA.

NDC 0069-0308-01.

Store TRAZIMERA vials in the refrigerator at 2°C to 8°C (36°F to 46°F) in the original carton to protect from light.

If needed, unopened TRAZIMERA vials may be removed from the refrigerator and stored at room temperature up to 30°C (86°F) for a single period of up to 3 months in the original carton to protect from light. Once removed from the refrigerator, do not return to the refrigerator and discard after 3 months or by the expiration date stamped on the vial, whichever occurs first. Write the revised expiration date in the space provided on the carton labeling.

17 PATIENT COUNSELING INFORMATION

Cardiomyopathy

- Advise patients to contact a health care professional immediately for any of the following: new onset or worsening shortness of breath, cough, swelling of the ankles/legs, swelling of the face, palpitations, weight gain of more than 5 pounds in 24 hours, dizziness or loss of consciousness [see Boxed Warning].

Embryo-Fetal Toxicity

- Advise pregnant women and females of reproductive potential that TRAZIMERA exposure during pregnancy or within 7 months prior to conception can result in fetal harm. Advise female patients to contact their healthcare provider with a known or suspected pregnancy [see Use in Specific Populations (8.1)].
- Advise females of reproductive potential to use effective contraception during treatment and for 7 months following the last dose of TRAZIMERA [see Use in Specific Populations (8.3)].

This product's labeling may have been updated. For the most recent prescribing information, please visit www.pfizer.com or www.TRAZIMERA.com.

For medical information about TRAZIMERA, please visit www.pfizermedinfo.com or call 1-800-438-1985.

Manufactured by:
Pfizer Ireland Pharmaceuticals
Cork, Ireland
US License No. 2060

Distributed by
Pfizer Labs
Division of Pfizer Inc.
New York, NY 10001

LAB-0995-6.0

PRINCIPAL DISPLAY PANEL - 420 mg Vial Label

NDC 0069-0306-01
Rx only

Trazimera™
(trastuzumab-qyyp)
For Injection

Mfg. by
Pfizer Ireland Pharmaceuticals
Cork, Ireland

US License No. 2060

420 mg/vial

For intravenous infusion after reconstitution

Multiple-dose vial

Reconstitution, Dosage, and Administration: For IV administration only.

See prescribing information for preparation instructions, dosage, and administration.

Storage: Refrigerate at 2°C to 8°C (36°F to 46°F). Unopened vial can be stored up to 30°C
(86°F) for a single period of up to 3 months but not exceeding the expiry date.

Reconstitute with 20 mL Bacteriostatic Water for Injection (1.1% benzyl alcohol) to yield a
21 mg/mL multiple-dose solution that delivers 20 mL (420 mg trastuzumab-qyyp). Store
reconstituted solution in refrigerator at 2°C to 8°C (36°F to 46°F). Do Not Freeze.
Do Not Shake After Reconstitution. Discard unused reconstituted solution after 28 days.

Discard after ____/____/____

PRINCIPAL DISPLAY PANEL - 20 mL Vial Label

BACTERIOSTATIC WATER FOR INJECTION

NOT FOR USE IN NEWBORNS
NDC 0069-0307-01

For Drug Diluent Use Only
Use 20 mL as DILUENT for reconstitution of
Trazimera

Each mL contains: 1.1% benzyl alcohol;
Water for Injection q.s. pH 4.5 to 8.0
See enclosed full prescribing information.
Use only if solution is clear and seal intact.
Sterile. Nonpyrogenic.

Store at controlled room temperature
2°C to 30°C (36°F to 86°F).

20 mL VIAL

PAA140335

PRINCIPAL DISPLAY PANEL - Kit Carton

NDC 0069-0305-01

Trazimera™
(trastuzumab-qyyp)
For Injection

420 mg/vial

For intravenous infusion after reconstitution

Multiple-dose vial

Rx only

Pfizer Oncology

PRINCIPAL DISPLAY PANEL - 150 mg Vial Label

NDC 0069-0308-01
Rx only

Trazimera™
(trastuzumab-qyyp)
For Injection

Mfg. by Pfizer Ireland
Pharmaceuticals
Cork, Ireland

US License No. 2060

150 mg/vial

For intravenous infusion after reconstitution
Single-dose vial

For Reconstitution, Dilution and Dosage: See Prescribing Information.

Storage: Refrigerate at 2°C to 8°C (36°F to 46°F) in the original carton
to protect from light. Unopened vial can be stored up to 30°C (86°F) for
a single period of up to 3 months but not exceeding the expiry date.
Discard after ____/____/____. Do Not Freeze. Do Not Shake After
Reconstitution. Discard unused reconstituted solution after 24 hours.

PRINCIPAL DISPLAY PANEL - 150 mg Vial Carton

NDC 0069-0308-01

Trazimera™
(trastuzumab-qyyp)

For Injection

150 mg/vial

For intravenous infusion after
reconstitution

Single-dose vial

Rx only

Pfizer Oncology